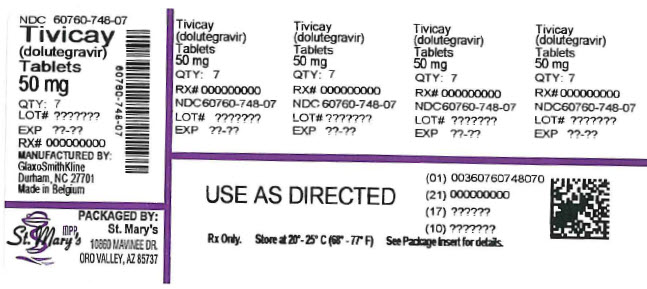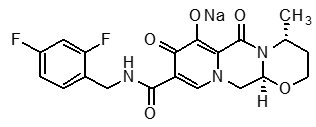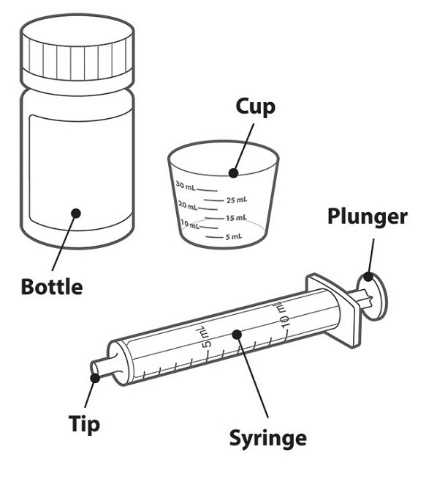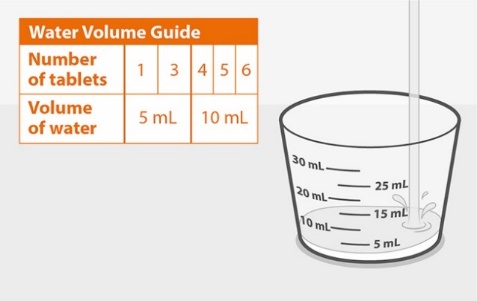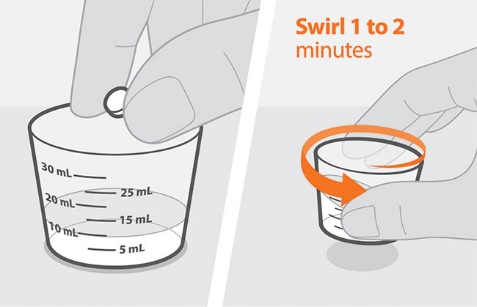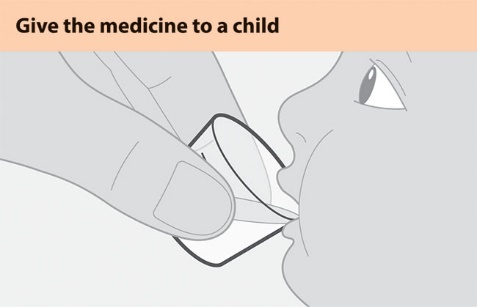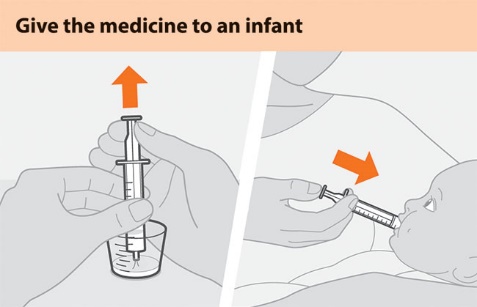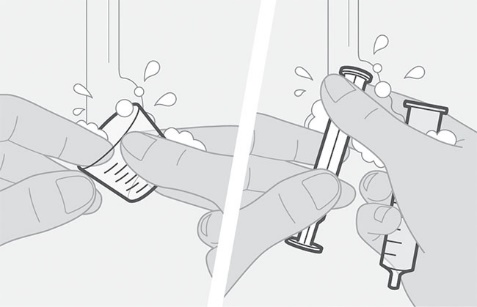 DRUG LABEL: Tivicay
NDC: 60760-748 | Form: TABLET, FILM COATED
Manufacturer: ST. MARY'S MEDICAL PARK PHARMACY
Category: prescription | Type: HUMAN PRESCRIPTION DRUG LABEL
Date: 20260114

ACTIVE INGREDIENTS: DOLUTEGRAVIR SODIUM 50 mg/1 1
INACTIVE INGREDIENTS: MANNITOL; MICROCRYSTALLINE CELLULOSE; POVIDONE, UNSPECIFIED; SODIUM STARCH GLYCOLATE TYPE A CORN; SODIUM STEARYL FUMARATE; FERRIC OXIDE YELLOW; POLYETHYLENE GLYCOL, UNSPECIFIED; POLYVINYL ALCOHOL, UNSPECIFIED; TALC; TITANIUM DIOXIDE

HIGHLIGHTS OF PRESCRIBING INFORMATION

These highlights do not include all the information needed to use TIVICAY safely and effectively. See full prescribing information for TIVICAY.
TIVICAY (dolutegravir) tablets, for oral use
TIVICAY PD (dolutegravir) tablets for oral suspension
Initial U.S. Approval: 2013

1 INDICATIONS AND USAGE

TIVICAY and TIVICAY PD are an HIV-1 integrase strand transfer inhibitor (INSTI) indicated in combination with other antiretroviral agents for the treatment of HIV-1 infection in adults (treatment-naïve or -experienced) and in pediatric patients (treatment-naïve or -experienced but INSTI- naïve) aged at least 4 weeks and weighing at least 3 kg. (1)

TIVICAY is indicated in combination with rilpivirine as a complete regimen for the treatment of HIV-1 infection in adults to replace the current antiretroviral regimen in those who are virologically suppressed (HIV-1 RNA less than 50 copies/mL) on a stable antiretroviral regimen for at least 6 months with no history of treatment failure or known substitutions associated with resistance to either antiretroviral agent. (1)

2 DOSAGE AND ADMINISTRATION

- May be taken without regard to food. (2.2, 2.6)

Adult Population | Recommended Dose
Treatment-naïve or treatment-experienced INSTI-naïve or virologically suppressed (HIV-1 RNA <50 copies per mL) adults switching to dolutegravir plus rilpivirinea(2.1) | 50 mg once daily
Treatment-naïve or treatment-experienced INSTI-naïve when coadministered with certain UGT1A or CYP3A inducers (2.1, 7.2, 7.3) | 50 mg twice daily
INSTI-experienced with certain INSTI-associated resistance substitutions or clinically suspected INSTI resistanceb(2.1, 12.4) | 50 mg twice daily
UGT = uridine diphosphate glucuronosyltransferase; CYP = cytochrome P450.
a Rilpivirine dose is 25 mg once daily for those switching to dolutegravir plus rilpivirine.
b Alternative combinations that do not include metabolic inducers should be considered where possible.

Pediatric Patients:Treatment-naïve or treatment-experienced INSTI-naïve patients aged at least 4 weeks and weighing at least 3 kg. See Tables 2, 3, and 4for complete pediatric dosing recommendations. (2.3, 2.4, 2.5). TIVICAY and TIVICAY PD are not bioequivalent and are not substitutable on a milligram-per-milligram basis.

Pediatric Population; Body Weight | Recommended Dosea; TIVICAY PD Tablets for Oral Suspension
3 kg to less than 6 kg | 5 mg once daily
6 kg to less than 10 kg | 15 mg once daily
10 kg to less than 14 kg | 20 mg once daily
14 kg to less than 20 kg | 25 mg once daily
20 kg and greater | 30 mg once daily
a If certain UGT1A or CYP3A inducers are coadministered, then adjust the weight-based dose of TIVICAY to twice daily. (2.3, 2.4, 7.2, 7.3)

Alternative dosing recommendations for TIVICAY tablets for patients weighing at least 14 kg (Table 4):

- 14 kg to less than 20 kg: 40 mg once daily.
- 20 kg and greater: 50 mg once daily.

3 DOSAGE FORMS AND STRENGTHS

- TIVICAY tablets: 10 mg, 25 mg, and 50 mg (3)
- TIVICAY PD tablets for oral suspension: 5 mg (3)

4 CONTRAINDICATIONS

- Previous hypersensitivity reaction to dolutegravir. (4)
- Coadministration with dofetilide. (4)

5 WARNINGS AND PRECAUTIONS

- Hypersensitivity reactions characterized by rash, constitutional findings, and sometimes organ dysfunction, including liver injury, have been reported. Discontinue TIVICAY or TIVICAY PD and other suspect agents immediately if signs or symptoms of hypersensitivity reactions develop, as a delay in stopping treatment may result in a life-threatening reaction. (5.1)
- Hepatotoxicity has been reported in patients receiving dolutegravir-containing regimens. Patients with underlying hepatitis B or C may be at increased risk for worsening or development of transaminase elevations. Monitoring for hepatotoxicity is recommended. (5.2)
- Immune reconstitution syndrome has been reported in patients treated with combination antiretroviral therapy. (5.4)
- TIVICAY tablets and TIVICAY PD tablets for oral suspension are not substitutable. (2.2, 5.5)

6 ADVERSE REACTIONS

The most common adverse reactions of moderate to severe intensity and incidence at least 2% (in those receiving TIVICAY in any one adult trial) are insomnia, fatigue, and headache. (6.1)

To report SUSPECTED ADVERSE REACTIONS, contact ViiV Healthcare at 1-877-844-8872 or FDA at 1-800-FDA-1088 or www.fda.gov/medwatch.

7 DRUG INTERACTIONS

- Refer to the full prescribing information for important drug interactions with TIVICAY or TIVICAY PD. (4, 7)
- Drugs that are metabolic inducers may decrease the plasma concentrations of dolutegravir. (7.2, 7.3)
- TIVICAY or TIVICAY PD should be taken 2 hours before or 6 hours after taking cation-containing antacids or laxatives, sucralfate, oral supplements containing iron or calcium, or buffered medications. When taken with food, TIVICAY and supplements containing calcium or iron can be taken at the same time. (7.3)

FULL PRESCRIBING INFORMATION

1 INDICATIONS AND USAGE

TIVICAY and TIVICAY PD are indicated in combination with other antiretroviral agents for the treatment of HIV‑1 infection in adults (treatment-naïve or -experienced) and in pediatric patients (treatment-naïve or -experienced but integrase strand transfer inhibitor [INSTI]-naïve) aged at least 4 weeks and weighing at least 3 kg [see Microbiology (12.4)].

TIVICAY is indicated in combination with rilpivirine as a complete regimen for the treatment of HIV-1 infection in adults to replace the current antiretroviral regimen in those who are virologically suppressed (HIV-1 RNA less than 50 copies/ mL) on a stable antiretroviral regimen for at least 6 months with no history of treatment failure or known substitutions associated with resistance to either antiretroviral agent.

2 DOSAGE AND ADMINISTRATION

2.1 Recommended Dosage in Adults

TIVICAY tablets may be taken with or without food.

Table 1. Dosing Recommendations for TIVICAY Tablets in Adult Patients
Population | Recommended Dosage
Treatment-naïve or treatment-experienced INSTI-naïve or virologically suppressed (HIV‑1 RNA <50 copies/mL) adults switching to dolutegravir plus rilpivirinea | 50 mg once daily
Treatment-naïve or treatment-experienced INSTI-naïve when coadministered with certain uridine diphosphate (UDP)-glucuronosyl transferase 1A1 (UGT1A) or cytochrome P450 (CYP)3A inducers [see Drug Interactions (7.2, 7.3)] | 50 mg twice daily
INSTI-experienced with certain INSTI-associated resistance substitutions or clinically suspected INSTI resistanceb [see Microbiology (12.4)] | 50 mg twice daily
INSTI = integrase strand transfer inhibitor.
a Rilpivirine dose is 25 mg once daily for those switching to dolutegravir plus rilpivirine.
b Alternative combinations that do not include metabolic inducers should be considered where possible [see Drug Interactions (7.3)] .

2.2 General Dosing and Administration Instructions for Pediatric Patients

Do not substitute TIVICAY tablets and TIVICAY PD tablets for oral suspension on a milligram-per-milligram basis due to differing pharmacokinetic profiles [see Warnings and Precautions (5.5), Clinical Pharmacology (12.3)]. If switching from the tablets to the tablets for oral suspension, follow the recommended dosage in Table 3. If switching from the tablets for oral suspension to the tablets, follow the recommended dosage in Table 4. See administration instructions in [Dosage and Administration (2.5)] .

2.3 Recommended Dosage in Pediatric Patients Weighing 3 to 14 kg

The recommended weight-based dosage of TIVICAY PD tablets for oral suspension in pediatric patients weighing 3 to 14 kg(4 weeks and older, treatment-naïve, or treatment-experienced but naïve to INSTI treatment) is described in Table 2.

Do not use TIVICAY tablets in patients weighing 3 to 14 kg. See administration instructions in [Dosage and Administration (2.5)] .

Table 2. Recommended Dosage of TIVICAY PD in Pediatric Patients 4 Weeks and Older Weighing 3 to 14 kg
Body Weight | TIVICAY PD Tablets for Oral Suspension
Body Weight | Daily Dosea | Number of; 5-mg Tablets
3 kg to less than 6 kg | 5 mg once daily | 1
6 kg to less than 10 kg | 15 mg once daily | 3
10 kg to less than 14 kg | 20 mg once daily | 4
a If certain uridine diphosphate glucuronosyltransferase (UGT)1A or cytochrome P450 (CYP)3A inducers are coadministered, then administer TIVICAY PD twice daily [see Drug Interactions (7.2, 7.3)] .

2.4 Recommended Dosage in Pediatric Patients Weighing 14 kg or Greater

For pediatric patients weighing 14 kg or greater(4 weeks and older, treatment-naïve, or treatment-experienced but naïve to INSTI treatment) administer either:

- TIVICAY PD tablets for oral suspension (preferred in pediatric patients weighing less than 20 kg) (Table 3), or
- TIVICAY tablets for oral use (Table 4)

Table 3. Recommended Dosage of TIVICAY PD Tablets for Oral Suspension in Pediatric Patients Weighing 14 kg or Greater
Body Weight | TIVICAY PD Tablets for Oral Suspension
Body Weight | Daily Dosea | Number of; 5-mg Tablets
14 kg to less than 20 kg | 25 mg once daily | 5
20 kg and greater | 30 mg once daily | 6
a If certain UGT1A or CYP3A inducers are coadministered, then administer TIVICAY PD twice daily [see Drug Interactions (7.2, 7.3)] .

Table 4. Recommended Dosage of TIVICAY Tablets in Pediatric Patients Weighing 14 kg or Greater
Body Weight | TIVICAY Tablets
Body Weight | Daily Dosea | Number of Tablets
14 kg to less than 20 kg | 40 mg once daily | 4 x 10-mg
20 kg and greater | 50 mg once daily | 1 x 50-mg
a If certain UGT1A or CYP3A inducers are coadministered, then administer TIVICAY twice daily [see Drug Interactions (7.2, 7.3)] .

2.5 Additional Administration Instructions

Administer TIVICAY tablets and TIVICAY PD tablets for oral suspension with or without food.

Administration Instructions for TIVICAY PD

Do not chew, cut, or crush TIVICAY PD [see Instructions for Use]. Instruct patients (or instruct caregivers) to either:

- Swallow the tablets for oral suspension whole (if more than one tablet is required, swallow one tablet at a time to reduce the risk of choking), or
- Fully disperse the tablets for oral suspension in 5 mL of drinking water (if using 1 or 3 tablets for oral suspension) or 10 mL (if using 4, 5, or 6 tablets for oral suspension) in the supplied cup; swirl the suspension so that no lumps remain. After full dispersion, administer the oral suspension within 30 minutes of mixing [see Instructions for Use].

3 DOSAGE FORMS AND STRENGTHS

TIVICAY Tablets:

10 mg: Each tablet contains 10 mg of dolutegravir (as dolutegravir sodium). Tablets are white, round, film-coated, biconvex tablets debossed with “SV 572” on one side and “10” on the other side.

25 mg: Each tablet contains 25 mg of dolutegravir (as dolutegravir sodium). Tablets are pale yellow, round, film-coated, biconvex tablets debossed with “SV 572” on one side and “25” on the other side.

50 mg: Each tablet contains 50 mg of dolutegravir (as dolutegravir sodium). Tablets are yellow, round, film-coated, biconvex tablets debossed with “SV 572” on one side and “50” on the other side.

TIVICAY PD Tablets for Oral Suspension:

Each tablet contains 5 mg of dolutegravir (as dolutegravir sodium). Tablets are white, round, strawberry cream flavored, film-coated, biconvex tablets debossed with “SV H7S” on one side and “5” on the other side.

4 CONTRAINDICATIONS

TIVICAY and TIVICAY PD are contraindicated in patients:

- with previous hypersensitivity reaction to dolutegravir [see Warnings and Precautions (5.1)].
- receiving dofetilide due to the potential for increased dofetilide plasma concentrations and the risk for serious and/or life-threatening events [see Drug Interactions (7)] .

5 WARNINGS AND PRECAUTIONS

5.1 Hypersensitivity Reactions

Hypersensitivity reactions have been reported and were characterized by rash, constitutional findings, and sometimes organ dysfunction, including liver injury. The events were reported in less than 1% of subjects receiving TIVICAY in Phase III clinical trials. Discontinue TIVICAY or TIVICAY PD and other suspect agents immediately if signs or symptoms of hypersensitivity reactions develop (including, but not limited to, severe rash or rash accompanied by fever, general malaise, fatigue, muscle or joint aches, blisters or peeling of the skin, oral blisters or lesions, conjunctivitis, facial edema, hepatitis, eosinophilia, angioedema, difficulty breathing). Clinical status, including liver aminotransferases, should be monitored and appropriate therapy initiated. Delay in stopping treatment with TIVICAY or TIVICAY PD or other suspect agents after the onset of hypersensitivity may result in a life-threatening reaction. TIVICAY and TIVICAY PD are contraindicated in patients who have experienced a previous hypersensitivity reaction to dolutegravir.

5.2 Hepatotoxicity

Hepatic adverse events have been reported in patients receiving a dolutegravir-containing regimen. Patients with underlying hepatitis B or C may be at increased risk for worsening or development of transaminase elevations with use of TIVICAY or TIVICAY PD [see Adverse Reactions (6.1)] . In some cases, the elevations in transaminases were consistent with immune reconstitution syndrome or hepatitis B reactivation particularly in the setting where anti-hepatitis therapy was withdrawn. Cases of hepatic toxicity, including elevated serum liver biochemistries, hepatitis, and acute liver failure have been reported in patients receiving a dolutegravir-containing regimen without pre-existing hepatic disease or other identifiable risk factors. Drug-induced liver injury leading to liver transplant has been reported with TRIUMEQ (abacavir, dolutegravir, and lamivudine). Monitoring for hepatotoxicity is recommended.

5.3 Risk of Adverse Reactions or Loss of Virologic Response Due to Drug Interactions

The concomitant use of TIVICAY or TIVICAY PD and other drugs may result in known or potentially significant drug interactions, some of which may lead to [see Contraindications (4), Drug Interactions (7.3)] :

- Loss of therapeutic effect of TIVICAY or TIVICAY PD and possible development of resistance.
- Possible clinically significant adverse reactions from greater exposures of concomitant drugs.

For concomitant drugs for which the interaction can be mitigated, please see Table 8for steps to prevent or manage these possible and known significant drug interactions, including dosing recommendations. Consider the potential for drug interactions prior to and during therapy with TIVICAY or TIVICAY PD; review concomitant medications during therapy with TIVICAY or TIVICAY PD; and monitor for the adverse reactions associated with the concomitant drugs.

5.4 Immune Reconstitution Syndrome

Immune reconstitution syndrome has been reported in patients treated with combination antiretroviral therapy, including TIVICAY or TIVICAY PD. During the initial phase of combination antiretroviral treatment, patients whose immune systems respond may develop an inflammatory response to indolent or residual opportunistic infections (such as Mycobacterium aviuminfection, cytomegalovirus, Pneumocystis jiroveciipneumonia [PCP], or tuberculosis), which may necessitate further evaluation and treatment.

Autoimmune disorders (such as Graves’ disease, polymyositis, and Guillain-Barré syndrome) have also been reported to occur in the setting of immune reconstitution; however, the time to onset is more variable and can occur many months after initiation of treatment.

5.5 Different Formulations Are Not Substitutable

TIVICAY and TIVICAY PD are not bioequivalent and are not substitutable on a milligram-per-milligram basis [see Clinical Pharmacology (12.3)] . If a pediatric patient switches from one formulation to the other, the dose must be adjusted for the new dosage formulation [see Dosage and Administration (2.2)] . Incorrect dosing of a given formulation may result in underdosing and loss of therapeutic effect and possible development of resistance or possible clinically significant adverse reactions from greater exposure of dolutegravir.

6 ADVERSE REACTIONS

The following serious adverse drug reactions are discussed in other sections of the labeling:

- Hypersensitivity reactions [see Warnings and Precautions (5.1)] .
- Hepatotoxicity [see Warnings and Precautions (5.2)].
- Immune Reconstitution Syndrome [see Warnings and Precautions (5.4)] .

6.1 Clinical Trials Experience

Because clinical trials are conducted under widely varying conditions, adverse reaction rates observed in the clinical trials of a drug cannot be directly compared with rates in the clinical trials of another drug and may not reflect the rates observed in practice.

Clinical Trials Experience in Adult Subjects

Treatment-Naïve Subjects:The safety assessment of TIVICAY in HIV‑1–infected treatment-naïve subjects is based on the analyses of data from 2 international, multicenter, double-blind trials, SPRING-2 (ING113086) and SINGLE (ING114467) and data from the international, multicenter, open-label FLAMINGO (ING114915) trial.

In SPRING-2, 822 subjects were randomized and received at least 1 dose of either TIVICAY 50 mg once daily or raltegravir 400 mg twice daily, both in combination with fixed-dose dual nucleoside reverse transcriptase inhibitor (NRTI) treatment (either abacavir sulfate and lamivudine [EPZICOM] or emtricitabine/tenofovir [TRUVADA]). There were 808 subjects included in the efficacy and safety analyses. Through 96 weeks, the rate of adverse events leading to discontinuation was 2% in both treatment arms.

In SINGLE, 833 subjects were randomized and received at least 1 dose of either TIVICAY 50 mg with fixed-dose abacavir sulfate and lamivudine (EPZICOM) once daily or fixed-dose efavirenz/emtricitabine/tenofovir (ATRIPLA) once daily (study treatment was blinded through Week 96 and open-label from Week 96 through Week 144). Through 144 weeks, the rates of adverse events leading to discontinuation were 4% in subjects receiving TIVICAY 50 mg once daily + EPZICOM and 14% in subjects receiving ATRIPLA once daily.

Treatment‑emergent adverse reactions of moderate to severe intensity observed in at least 2% of subjects in either treatment arm in SPRING-2 and SINGLE trials are provided in Table 5. Side-by-side tabulation is to simplify presentation; direct comparisons across trials should not be made due to differing trial designs.

Table 5. Treatment-Emergent Adverse Reactions of at Least Moderate Intensity (Grades 2 to 4) and at Least 2% Frequency in Treatment-Naïve Subjects in SPRING-2 (Week 96 Analysis) and SINGLE Trials (Week 144 Analysis)
System Organ Class/; Preferred Term | SPRING-2 |  | SINGLE
System Organ Class/; Preferred Term | TIVICAY; 50 mg Once Daily + 2 NRTIs; (n = 403) | Raltegravir; 400 mg Twice Daily + 2 NRTIs; (n = 405) | TIVICAY; 50 mg + EPZICOM Once Daily; (n = 414) | ATRIPLA; Once Daily; (n = 419)
Psychiatric
Insomnia | <1% | <1% | 3% | 3%
Depression | <1% | <1% | 1% | 2%
Abnormal dreams | <1% | <1% | <1% | 2%
Nervous System
Dizziness | <1% | <1% | <1% | 5%
Headache | <1% | <1% | 2% | 2%
Gastrointestinal
Nausea | 1% | 1% | <1% | 3%
Diarrhea | <1% | <1% | <1% | 2%
Skin and Subcutaneous Tissue
Rasha | 0 | <1% | <1% | 6%
General Disorders
Fatigue | <1% | <1% | 2% | 2%
Ear and Labyrinth
Vertigo | 0 | <1% | 0 | 2%
NRTI = Nucleoside Reverse Transcriptase Inhibitor.
a Includes pooled terms: rash, rash generalized, rash macular, rash maculo-papular, rash pruritic, and drug eruption.

In addition, Grade 1 insomnia was reported by 1% and less than 1% of subjects receiving TIVICAY and raltegravir, respectively, in SPRING-2; whereas in SINGLE the rates were 7% and 4% for TIVICAY and ATRIPLA, respectively. These events were not treatment limiting.

In a multicenter, open-label trial (FLAMINGO), 243 subjects received TIVICAY 50 mg once daily versus 242 subjects who received darunavir 800 mg/ritonavir 100 mg once daily, both in combination with investigator-selected NRTI background regimen (either EPZICOM or TRUVADA). There were 484 subjects included in the efficacy and safety analyses. Through 96 weeks, the rates of adverse events leading to discontinuation were 3% in subjects receiving TIVICAY and 6% in subjects receiving darunavir/ritonavir. The adverse reactions observed in FLAMINGO were generally consistent with those seen in SPRING-2 and SINGLE.

Treatment-Experienced, Integrase Strand Transfer Inhibitor-Naïve Subjects:In an international, multicenter, double-blind trial (ING111762, SAILING), 719 HIV‑1–infected, antiretroviral treatment-experienced adults were randomized and received either TIVICAY 50 mg once daily or raltegravir 400 mg twice daily with investigator-selected background regimen consisting of up to 2 agents, including at least one fully active agent. At 48 weeks, the rates of adverse events leading to discontinuation were 3% in subjects receiving TIVICAY 50 mg once daily + background regimen and 4% in subjects receiving raltegravir 400 mg twice daily + background regimen.

The only treatment‑emergent adverse reaction of moderate to severe intensity with at least 2% frequency in either treatment group was diarrhea, 2% (6 of 354) in subjects receiving TIVICAY 50 mg once daily + background regimen and 1% (5 of 361) in subjects receiving raltegravir 400 mg twice daily + background regimen.

Treatment-Experienced, Integrase Strand Transfer Inhibitor-Experienced Subjects:In a multicenter, open-label, single‑arm trial (ING112574, VIKING-3), 183 HIV‑1–infected, antiretroviral treatment-experienced adults with virological failure and current or historical evidence of raltegravir and/or elvitegravir resistance received TIVICAY 50 mg twice daily with the current failing background regimen for 7 days and with optimized background therapy from Day 8. The rate of adverse events leading to discontinuation was 4% of subjects at Week 48.

Treatment‑emergent adverse reactions in VIKING-3 were generally similar compared with observations with the 50-mg once-daily dose in adult Phase III trials.

Virologically Suppressed Subjects:The adverse reactions observed for TIVICAY plus rilpivirine in the Week 48 analysis of pooled data from 2 identical, international, multicenter, open-label trials (SWORD-1 and SWORD-2) of 513 HIV-1–infected, virologically suppressed subjects switching from their current antiretroviral regimen to TIVICAY plus rilpivirine, were consistent with the adverse reaction profiles and severities for the individual components when administered with other antiretroviral agents. There were no adverse reactions (Grades 2 to 4) with an incidence of at least 2% in either treatment arm at Week 48. The safety profile during the additional follow-up period through Week 148 were consistent with Week 48. The rate of adverse events leading to discontinuation through Week 48 was 4% in subjects receiving TIVICAY plus rilpivirine once daily and less than 1% in subjects who remained on their current antiretroviral regimen. In the pooled analyses, the proportion of subjects receiving TIVICAY plus rilpivirine who discontinued treatment due to an adverse event through Week 148 was 8%.

Less Common Adverse Reactions Observed in Treatment-Naïve and Treatment-Experienced Trials:The following adverse reactions occurred in less than 2% of treatment-naïve or treatment-experienced subjects receiving TIVICAY in a combination regimen in any one trial. These events have been included because of their seriousness and assessment of potential causal relationship.

Gastrointestinal Disorders:Abdominal pain, abdominal discomfort, flatulence, upper abdominal pain, vomiting.

Hepatobiliary Disorders:Hepatitis.

Musculoskeletal Disorders:Myositis.

Psychiatric Disorders:Suicidal ideation, attempt, behavior, or completion. These events were observed primarily in subjects with a pre-existing history of depression or other psychiatric illness.

Renal and Urinary Disorders:Renal impairment.

Skin and Subcutaneous Tissue Disorders:Pruritus.

Laboratory Abnormalities:

Treatment-Naïve Subjects:Selected laboratory abnormalities (Grades 2 to 4) with a worsening grade from baseline and representing the worst-grade toxicity in at least 2% of subjects are presented in Table 6. The mean change from baseline observed for selected lipid values is presented in Table 7. Side-by-side tabulation is to simplify presentation; direct comparisons across trials should not be made due to differing trial designs.

Table 6. Selected Laboratory Abnormalities (Grades 2 to 4) in Treatment-Naïve Subjects in SPRING-2 (Week 96 Analysis) and SINGLE Trials (Week 144 Analysis)
Laboratory Parameter; Preferred Term | SPRING-2 |  | SINGLE
Laboratory Parameter; Preferred Term | TIVICAY 50 mg Once Daily + 2 NRTIs; (n = 403) | Raltegravir; 400 mg Twice Daily + 2 NRTIs; (n = 405) | TIVICAY 50 mg + EPZICOM Once Daily; (n = 414) | ATRIPLA; Once Daily; (n = 419)
ALT
Grade 2 (>2.5-5.0 x ULN) | 4% | 4% | 3% | 5%
Grade 3 to 4 (>5.0 x ULN) | 2% | 2% | 1% | <1%
AST
Grade 2 (>2.5-5.0 x ULN) | 5% | 3% | 3% | 4%
Grade 3 to 4 (>5.0 x ULN) | 3% | 2% | 1% | 3%
Total Bilirubin
Grade 2 (1.6-2.5 x ULN) | 3% | 2% | <1% | <1%
Grade 3 to 4 (>2.5 x ULN) | <1% | <1% | <1% | <1%
Creatine kinase
Grade 2 (6.0-9.9 x ULN) | 2% | 5% | 5% | 3%
Grade 3 to 4 (≥10.0 x ULN) | 7% | 4% | 7% | 8%
Hyperglycemia
Grade 2 (126 250 mg/dL) | 6% | 6% | 9% | 6%
Grade 3 (>250 mg/dL) | <1% | 2% | 2% | <1%
Lipase
Grade 2 (>1.5-3.0 x ULN) | 7% | 7% | 11% | 11%
Grade 3 to 4 (>3.0 x ULN) | 2% | 5% | 5% | 4%
Total neutrophils
Grade 2 (0.75-0.99 x 10^9) | 4% | 3% | 4% | 5%
Grade 3 to 4 (<0.75 x 10^9) | 2% | 2% | 3% | 3%
ALT = Alanine aminotransferase; AST = Aspartate aminotransferase; NRTI = Nucleoside Reverse Transcriptase Inhibitor; ULN = Upper limit of normal.

Table 7. Mean Change from Baseline in Fasted Lipid Values in Treatment-Naïve Subjects in SPRING-2 (Week 96 Analysisa) and SINGLE Trials (Week 144 Analysisa)
Laboratory Parameter; Preferred Term | SPRING-2 |  | SINGLE
Laboratory Parameter; Preferred Term | TIVICAY; 50 mg Once Daily + 2 NRTIs; (n = 403) | Raltegravir; 400 mg Twice Daily + 2 NRTIs; (n = 405) | TIVICAY; 50 mg + EPZICOM Once Daily; (n = 414) | ATRIPLA; Once Daily; (n = 419)
Cholesterol (mg/dL) | 8.1 | 10.1 | 24.0 | 26.7
HDL cholesterol (mg/dL) | 2.0 | 2.3 | 5.4 | 7.2
LDL cholesterol (mg/dL) | 5.1 | 6.1 | 16.0 | 14.6
Triglycerides (mg/dL) | 6.7 | 6.6 | 13.6 | 31.9
HDL = High density lipoprotein; LDL = Low density lipoprotein; NRTI = Nucleoside Reverse Transcriptase Inhibitor.
a Subjects on lipid-lowering agents at baseline were excluded from these analyses (19 subjects in each arm in SPRING-2, and in SINGLE: TIVICAY + EPZICOM n = 30 and ATRIPLA n = 27). Ninety-four subjects initiated a lipid-lowering agent post-baseline; their last fasted on-treatment values (prior to starting the agent) were used regardless of whether they discontinued the agent (SPRING-2: TIVICAY n = 9, raltegravir n = 13; SINGLE: TIVICAY + EPZICOM n = 36, ATRIPLA n = 36).

Laboratory abnormalities observed in the FLAMINGO trial were generally consistent with observations in SPRING-2 and SINGLE.

Treatment-Experienced, Integrase Strand Transfer Inhibitor-Naïve Subjects:Laboratory abnormalities observed in SAILING were generally similar compared with observations seen in the treatment-naïve (SPRING-2 and SINGLE) trials.

Treatment-Experienced, Integrase Strand Transfer Inhibitor-Experienced Subjects:The most common treatment-emergent laboratory abnormalities (greater than 5% for Grades 2 to 4 combined) observed in VIKING-3 at Week 48 were elevated ALT (9%), AST (8%), cholesterol (10%), creatine kinase (6%), hyperglycemia (14%), and lipase (10%). Two percent (4 of 183) of subjects had a Grade 3 to 4 treatment-emergent hematology laboratory abnormality, with neutropenia (2% [3 of 183]) being the most frequently reported.

Virologically Suppressed Adults:Laboratory abnormalities observed in SWORD-1 and SWORD-2 were generally similar compared with observations seen in the other Phase III trials.

Hepatitis B and/or Hepatitis C Virus Co-infection:In Phase III trials, subjects with hepatitis B and/or C virus co-infection were permitted to enroll provided that baseline liver chemistry tests did not exceed 5 times the upper limit of normal. Overall, the safety profile in subjects with hepatitis B and/or C virus co-infection was similar to that observed in subjects without hepatitis B or C co-infection, although the rates of AST and ALT abnormalities were higher in the subgroup with hepatitis B and/or C virus co-infection for all treatment groups. Grades 2 to 4 ALT abnormalities in hepatitis B and/or C co-infected compared with HIV mono-infected subjects receiving TIVICAY were observed in 18% vs. 3% with the 50-mg once-daily dose and 13% vs. 8% with the 50-mg twice-daily dose. Liver chemistry elevations consistent with immune reconstitution syndrome were observed in some subjects with hepatitis B and/or C at the start of therapy with TIVICAY, particularly in the setting where anti-hepatitis therapy was withdrawn [see Warnings and Precautions (5.2)] .

Changes in Serum Creatinine:Dolutegravir has been shown to increase serum creatinine due to inhibition of tubular secretion of creatinine without affecting renal glomerular function [see Clinical Pharmacology (12.2)] . Increases in serum creatinine occurred within the first 4 weeks of treatment and remained stable through 96 weeks. In treatment-naïve subjects, a mean change from baseline of 0.15 mg/dL (range: -0.32 mg/dL to 0.65 mg/dL) was observed after 96 weeks of treatment. Creatinine increases were comparable by background NRTIs and were similar in treatment-experienced subjects.

Clinical Trials Experience in Pediatric Subjects

The safety and pharmacokinetics of TIVICAY and TIVICAY PD in HIV-1–infected pediatric subjects aged at least 4 weeks and weighing at least 3 kg was evaluated in the IMPAACT P1093 trial and 2 weight-band-based pharmacokinetic substudies of the ODYSSEY trial [see Use in Specific Populations (8.4), Clinical Pharmacology (12.3)] . Overall, the safety data in these pediatric studies were similar to those seen in adults, and there was no clinically significant difference in dolutegravir exposure [see Clinical Pharmacology (12.3)] .

IMPAACT P1093 is an ongoing, multicenter, open-label, non-comparative trial of HIV‑1–infected pediatric subjects aged 4 weeks to less than 18 years [see Use in Specific Populations (8.4), Clinical Pharmacology (12.3), Clinical Studies (14.3)] .

The safety analysis based on subjects (n = 75) who received the recommended dose (determined by weight and age) through Week 24 showed that 11% of subjects experienced drug-related clinical adverse reactions. The only Grade 1 to 2 drug-related clinical adverse reactions reported by more than one subject was immune reconstitution inflammatory syndrome (IRIS) (n = 2). There were no Grade 3 or 4 drug-related adverse reactions reported. No adverse reactions led to discontinuation.

The Grade 3 or 4 laboratory abnormalities reported in more than one subject were decreased neutrophil count (n = 11), decreased blood bicarbonate (n = 4), decreased hemoglobin (n = 3), increased lipase (n = 2), and increased blood potassium (n = 2). These laboratory events were not considered to be drug-related. Median laboratory values were similar at baseline and Week 24. Changes in median serum creatinine were similar to those observed in adults.

6.2 Postmarketing Experience

In addition to adverse reactions reported from clinical trials, the following adverse reactions have been identified during postmarketing use. Because these reactions are reported voluntarily from a population of uncertain size, it is not always possible to reliably estimate their frequency or establish a causal relationship to drug exposure.

Blood and Lymphatic Systems

Sideroblastic anemia.

Hepatobiliary Disorders

Acute liver failure, hepatotoxicity.

Investigations

Weight increased.

Musculoskeletal

Arthralgia, myalgia.

Psychiatric

Anxiety.

7 DRUG INTERACTIONS

7.1 Effect of Dolutegravir on the Pharmacokinetics of Other Agents

In vitro, dolutegravir inhibited the renal organic cation transporters, OCT2 (IC50 = 1.93 microM) and multidrug and toxin extrusion transporter (MATE) 1 (IC50 = 6.34 microM). In vivo, dolutegravir inhibits tubular secretion of creatinine by inhibiting OCT2 and potentially MATE1. Dolutegravir may increase plasma concentrations of drugs eliminated via OCT2 or MATE1 (dofetilide, dalfampridine, and metformin, Table 8) [see Contraindications (4), Drug Interactions (7.3)] .

In vitro, dolutegravir inhibited the basolateral renal transporters, organic anion transporter (OAT) 1 (IC50 = 2.12 microM) and OAT3 (IC50 = 1.97 microM). However, in vivo, dolutegravir did not alter the plasma concentrations of tenofovir or para-amino hippurate, substrates of OAT1 and OAT3.

In vitro, dolutegravir did not inhibit (IC50greater than 50 microM) the following: cytochrome P450 (CYP)1A2, CYP2A6, CYP2B6, CYP2C8, CYP2C9, CYP2C19, CYP2D6, CYP3A, uridine diphosphate glucuronosyltransferase (UGT)1A1, UGT2B7, P-glycoprotein (P-gp), breast cancer resistance protein (BCRP), bile salt export pump (BSEP), organic anion transporter polypeptide (OATP)1B1, OATP1B3, OCT1, multidrug resistance protein (MRP)2, or MRP4. In vitro, dolutegravir did not induce CYP1A2, CYP2B6, or CYP3A4. Based on these data and the results of drug interaction trials, dolutegravir is not expected to affect the pharmacokinetics of drugs that are substrates of these enzymes or transporters.

7.2 Effect of Other Agents on the Pharmacokinetics of Dolutegravir

Dolutegravir is metabolized by UGT1A1 with some contribution from CYP3A. Dolutegravir is also a substrate of UGT1A3, UGT1A9, BCRP, and P-gp in vitro. Drugs that induce those enzymes and transporters may decrease dolutegravir plasma concentration and reduce the therapeutic effect of dolutegravir.

Coadministration of dolutegravir and other drugs that inhibit these enzymes may increase dolutegravir plasma concentration.

Etravirine significantly reduced plasma concentrations of dolutegravir, but the effect of etravirine was mitigated by coadministration of lopinavir/ritonavir or darunavir/ritonavir and is expected to be mitigated by atazanavir/ritonavir (Table 8) [see Drug Interactions (7.3), Clinical Pharmacology (12.3)] .

In vitro, dolutegravir was not a substrate of OATP1B1 or OATP1B3.

7.3 Established and Other Potentially Significant Drug Interactions

Table 8provides clinical recommendations as a result of drug interactions with TIVICAY or TIVICAY PD. These recommendations are based on either drug interaction trials or predicted interactions due to the expected magnitude of interaction and potential for serious adverse events or loss of efficacy [s ee Dosage and Administration (2), Clinical Pharmacology (12.3)].

Table 8. Established and Other Potentially Significant Drug Interactions: Alterations in Dose or Regimen May Be Recommended Based on Drug Interaction Trials or Predicted Interactions [see Dosage and Administration (2)]
Concomitant Drug Class: Drug Name | Effect on Concentration of Dolutegravir and/or Concomitant Drug | Clinical Comment
HIV-1 Antiviral Agents
Non-nucleoside reverse transcriptase inhibitor:; Etravirinea | ↓Dolutegravir | Use of TIVICAY or TIVICAY PD with etravirine without coadministration of atazanavir/ritonavir, darunavir/ritonavir, or lopinavir/ritonavir is not recommended.
Non-nucleoside reverse transcriptase inhibitor:; Efavirenza | ↓Dolutegravir | Adjust dose of TIVICAY to twice daily for treatment-naïve and treatment-experienced, INSTI-naïve adult patients.; In pediatric patients, increase the weight-based dose of TIVICAY or TIVICAY PD to twice daily (Tables 2, 3, and 4).; Use alternative combinations that do not include metabolic inducers where possible for INSTI-experienced patients with certain INSTI-associated resistance substitutions or clinically suspected INSTI resistance.b
Non-nucleoside reverse transcriptase inhibitor:; Nevirapine | ↓Dolutegravir | Avoid coadministration with nevirapine because there are insufficient data to make dosing recommendations.
Protease inhibitors:; Fosamprenavir/ritonavira; Tipranavir/ritonavira | ↓Dolutegravir | Adjust dose of TIVICAY to twice daily for treatment-naïve and treatment-experienced, INSTI-naïve adult patients.; In pediatric patients, increase the weight-based dose of TIVICAY or TIVICAY PD to twice daily (Tables 2, 3, and 4).; Use alternative combinations that do not include metabolic inducers where possible for INSTI-experienced patients with certain INSTI-associated resistance substitutions or clinically suspected INSTI resistance.b
Other Agents
Dofetilide | ↑Dofetilide | Coadministration is contraindicated with TIVICAY or TIVICAY PD [see Contraindications (4)] .
Carbamazepinea | ↓Dolutegravir | Adjust dose of TIVICAY to twice daily in treatment-naïve or treatment-experienced, INSTI-naïve adult patients.; In pediatric patients, increase the weight-based dose of TIVICAY or TIVICAY PD to twice daily (Tables 2, 3, and 4).; Use alternative treatment that does not include carbamazepine where possible for INSTI-experienced patients with certain INSTI-associated resistance substitutions or clinically suspected INSTI resistance.b
Oxcarbazepine Phenytoin Phenobarbital St. John’s wort (Hypericum perforatum) | ↓Dolutegravir | Avoid coadministration with TIVICAY or TIVICAY PD because there are insufficient data to make dosing recommendations.
Medications containing polyvalent cations (e.g., Mg or Al):; Cation-containing antacidsaor laxatives Sucralfate Buffered medications | ↓Dolutegravir | Administer TIVICAY or TIVICAY PD 2 hours before or 6 hours after taking medications containing polyvalent cations.
Oral calcium or iron supplements, including multivitamins containing calcium or irona | ↓Dolutegravir | When taken with food, TIVICAY and supplements or multivitamins containing calcium or iron can be taken at the same time. Under fasting conditions, TIVICAY or TIVICAY PD should be taken 2 hours before or 6 hours after taking supplements containing calcium or iron.
Potassium channel blocker:; Dalfampridine | ↑Dalfampridine | Elevated levels of dalfampridine increase the risk of seizures. The potential benefits of taking dalfampridine concurrently with TIVICAY or TIVICAY PD should be considered against the risk of seizures in these patients.
Metformin | ↑Metformin | Refer to the prescribing information for metformin for assessing the benefit and risk of concomitant use of TIVICAY or TIVICAY PD and metformin.
Rifampina | ↓Dolutegravir | Adjust dose of TIVICAY to twice daily for treatment-naïve and treatment-experienced, INSTI-naïve adult patients.; In pediatric patients, increase the weight-based dose of TIVICAY or TIVICAY PD to twice daily (Tables 2, 3, and 4).; Use alternatives to rifampin where possible for INSTI-experienced patients with certain INSTI-associated resistance substitutions or clinically suspected INSTI resistance.b
INSTI = integrase strand transfer inhibitor.
a See Clinical Pharmacology (12.3) Table 11or Table 12for magnitude of interaction.
b The lower dolutegravir exposures observed in INSTI-experienced patients (with certain INSTI-associated resistance substitutions or clinically suspected INSTI resistance [see Microbiology (12.4)]) upon coadministration with certain inducers may result in loss of therapeutic effect and development of resistance to TIVICAY or other coadministered antiretroviral agents.

7.4 Drugs without Clinically Significant Interactions with Dolutegravir

Based on drug interaction trial results, the following drugs can be coadministered with dolutegravir without a dose adjustment: atazanavir/ritonavir, darunavir/ritonavir, elbasvir/grazoprevir, methadone, midazolam, omeprazole, oral contraceptives containing norgestimate and ethinyl estradiol, prednisone, rifabutin, rilpivirine, sofosbuvir/velpatasvir, and tenofovir [see Clinical Pharmacology (12.3)] .

8 USE IN SPECIFIC POPULATIONS

8.1 Pregnancy

Pregnancy Exposure Registry

There is a pregnancy exposure registry that monitors pregnancy outcomes in individuals exposed to TIVICAY or TIVICAY PD during pregnancy. Healthcare providers are encouraged to register patients by calling the Antiretroviral Pregnancy Registry (APR) at 1-800-258-4263.

Risk Summary

Data from two, ongoing birth outcome surveillance studies in Botswana and Eswatini which together include over 14,000 individuals evaluated during pregnancy show similar prevalence of neural tube defects among infants born to individuals taking dolutegravir at the time of conception compared to those born to individuals taking non-dolutegravir-containing regimens at conception or infants born to HIV-negative individuals. (see Data).

There are insufficient human data on the use of dolutegravir during pregnancy to definitively assess a drug-associated risk for birth defects and miscarriage. However, available human data from the APR do not indicate an increased risk of birth defects (see Data). The background risk for major birth defects for the indicated population is unknown. In the U.S. general population, the estimated background rate for major birth defects and miscarriage in clinically recognized pregnancies is 2% to 4% and 15% to 20%, respectively.

In animal reproduction studies, no evidence of adverse developmental outcomes (including neural tube defects) was observed with dolutegravir at systemic exposures (AUC) less than (rabbits) and approximately 27 times (rats) the exposure in humans at the maximum recommended human dose (MRHD) of TIVICAY (see Data).

Data

Human Data:

Observational studies:The first interim analysis from an ongoing birth outcome surveillance study in Botswana identified an association between dolutegravir and an increased risk of neural tube defects when dolutegravir was administered at the time of conception and in early pregnancy. A subsequent analysis was conducted based on a larger cohort from the birth outcome surveillance study in Botswana and included over 9,460 individuals exposed to dolutegravir at conception, 23,664 individuals exposed to non-dolutegravir-containing regimens, and 170,723 HIV-negative pregnant individuals. The prevalence of neural tube defects in infants delivered to individuals taking dolutegravir at conception was 0.11% (95% CI: 0.05-0.19%). The observed prevalence rate did not differ significantly from that of infants delivered to individuals taking non-dolutegravir-containing regimens (0.11%, 95% CI: 0.07-0.16%), or to HIV-negative individuals (0.06%, 95% CI: 0.05-0.08%).

The Eswatini birth outcome surveillance study includes 9,743 individuals exposed to dolutegravir at conception, 1,838 individuals exposed to non-dolutegravir-containing regimens, and 32,259 HIV-negative pregnant individuals. The prevalence of neural tube defects in infants delivered to individuals taking dolutegravir at conception was 0.08% (95% CI: 0.04-0.16%). The observed prevalence rate did not differ significantly from that of infants delivered to individuals taking non-dolutegravir-containing regimens (0.22%, 95% CI: 0.06-0.56%) or to HIV-negative individuals (0.08%, 95% CI: 0.06-0.12%). The observed prevalence of neural tube defects in infants delivered to individuals taking non-dolutegravir-containing regimens had a wide confidence interval due to low sample size.

Limitations of these birth outcome surveillance studies include insufficient data to determine if baseline characteristics were balanced between the study groups or to assess other factors such as the use of folic acid during the preconception or first trimester periods.

Antiretroviral Pregnancy Registry:Based on prospective reports to the APR, of 1,377 exposures to dolutegravir during pregnancy resulting in live births (including 874 exposed in the first trimester), the prevalence of defects in live births was 3.3% (95% CI: 2.2% to 4.7%) following first-trimester exposure to dolutegravir-containing regimens and 5.0% (95% CI: 3.2% to 7.3%) following second-/third-trimester exposure to dolutegravir-containing regimens. In the U.S. reference population of the Metropolitan Atlanta Congenital Defects Program (MACDP), the background birth defect rate was 2.7%.

Dolutegravir has been shown to cross the placenta. In a clinical trial in Uganda and South Africa in women during the last trimester of pregnancy receiving dolutegravir 50 mg once daily, the ratio of median dolutegravir concentration in fetal umbilical cord to that in maternal peripheral plasma was 1.21 (range 0.51 to 2.11) (n = 15).

Animal Data:

Dolutegravir was administered orally at up to 1,000 mg/kg daily to pregnant rats and rabbits on Gestation Days 6 to 17 and 6 to 18, respectively, and to rats on Gestation Day 6 to Lactation/Postpartum Day 20. No adverse effects on embryo-fetal (rats and rabbits) or pre/postnatal (rats) development were observed at up to the highest dose tested. During organogenesis, systemic exposures (AUC) to dolutegravir in rabbits were less than the exposure in humans at the MRHD and in rats were approximately 27 times the exposure in humans at the MRHD. In the rat pre/postnatal development study, decreased body weight of the developing offspring was observed during lactation at a maternally toxic dose (approximately 27 times human exposure at the MRHD).

8.2 Lactation

Risk Summary

Dolutegravir is present in human milk. It is not known whether dolutegravir affects human milk production or has effects on the breastfed infant.

Potential risks of breastfeeding include: (1) HIV‑1 transmission (in HIV-1–negative infants), (2) developing viral resistance (in HIV-1–positive infants), and (3) adverse reactions in a breastfed infant similar to those seen in adults.

8.4 Pediatric Use

The safety, pharmacokinetics, and effectiveness of TIVICAY and TIVICAY PD were evaluated in 75 HIV-1–infected, treatment-naïve or treatment-experienced, INSTI-naïve pediatric and adolescent subjects aged 4 weeks to less than 18 years weighing at least 3 kg in an ongoing, open-label, multicenter, dose-finding clinical trial, IMPAACT P1093 [see Adverse Reactions (6.1), Clinical Pharmacology (12.3), Clinical Studies (14.3)] . Additional pharmacokinetics data were evaluated in 2 pharmacokinetic substudies in ODYSSEY, an ongoing open-label, randomized, non-inferiority trial to evaluate the safety, efficacy, and pharmacokinetic parameters of TIVICAY or TIVICAY PD plus two NRTIs compared with standard of care in HIV-1–infected pediatric subjects younger than 18 years [see Clinical Pharmacology (12.3)] .

Overall, the safety data in pediatric subjects from the IMPAACT P1093 trial were comparable to those observed in adults [see Adverse Reactions (6.1)] . The pharmacokinetic parameters of TIVICAY or TIVICAY PD in pediatric subjects from IMPAACT P1093 and ODYSSEY were comparable to those of adults receiving 50 mg once daily or twice daily [see Clinical Pharmacology (12.3)] . The effectiveness observed in IMPAACT P1093 is comparable to that of treatment-experienced adult subjects.

Safety and effectiveness of TIVICAY or TIVICAY PD have not been established in pediatric patients aged less than 4 weeks or weighing less than 3 kg or in any pediatric patients who are INSTI-experienced with documented or clinically suspected resistance to other INSTIs (e.g., raltegravir, elvitegravir).

8.5 Geriatric Use

Clinical trials of TIVICAY did not include sufficient numbers of subjects aged 65 and older to determine whether they respond differently from younger subjects. In general, caution should be exercised in the administration of TIVICAY in elderly patients reflecting the greater frequency of decreased hepatic, renal, or cardiac function, and of concomitant disease or other drug therapy [see Clinical Pharmacology (12.3)] .

8.6 Hepatic Impairment

No clinically important pharmacokinetic differences between subjects with moderate hepatic impairment and matching healthy subjects were observed. No dosage adjustment is necessary for patients with mild to moderate hepatic impairment (Child-Pugh Score A or B). The effect of severe hepatic impairment (Child-Pugh Score C) on the pharmacokinetics of dolutegravir has not been studied. Therefore, TIVICAY and TIVICAY PD are not recommended for use in patients with severe hepatic impairment [see Clinical Pharmacology (12.3)] .

8.7 Renal Impairment

Dolutegravir plasma concentrations were decreased in subjects with severe renal impairment compared with those in matched healthy controls. However, no dosage adjustment is necessary for treatment-naïve or treatment-experienced and INSTI-naïve patients with mild, moderate, or severe renal impairment or for INSTI-experienced patients (with certain INSTI-associated resistance substitutions or clinically suspected INSTI resistance) with mild or moderate renal impairment. Caution is warranted for INSTI-experienced patients (with certain INSTI-associated resistance substitutions or clinically suspected INSTI resistance [see Microbiology (12.4)]) with severe renal impairment, as the decrease in dolutegravir concentrations may result in loss of therapeutic effect and development of resistance to TIVICAY, TIVICAY PD, or other coadministered antiretroviral agents [see Clinical Pharmacology (12.3)] . There is inadequate information to recommend appropriate dosing of dolutegravir in patients requiring dialysis.

10 OVERDOSAGE

There is no known specific treatment for overdose with TIVICAY or TIVICAY PD. If overdose occurs, the patient should be monitored, and standard supportive treatment applied as required. As dolutegravir is highly bound to plasma proteins, it is unlikely that it will be significantly removed by dialysis.

11 DESCRIPTION

TIVICAY contains dolutegravir, as dolutegravir sodium, an HIV INSTI. The chemical name of dolutegravir sodium is sodium (4 R,12a S)-9-{[(2,4-difluorophenyl)methyl]carbamoyl}-4-methyl-6,8-dioxo-3,4,6,8,12,12a-hexahydro-2 H-pyrido[1',2':4,5]pyrazino[2,1- b][1,3]oxazin-7-olate. The empirical formula is C20H18F2N3NaO5,and the molecular weight is 441.36 g/mol. It has the following structural formula:

Dolutegravir sodium is a white to light yellow powder and is slightly soluble in water.

Each film-coated tablet of TIVICAY for oral administration contains 10.5, 26.3, or 52.6 mg of dolutegravir sodium, which is equivalent to 10, 25, or 50 mg dolutegravir free acid, respectively, and the following inactive ingredients: D-mannitol, microcrystalline cellulose, povidone K29/32, sodium starch glycolate, and sodium stearyl fumarate. The tablet film‑coating contains the inactive ingredients iron oxide yellow (25-mg and 50-mg tablets only), macrogol/PEG, polyvinyl alcohol-part hydrolyzed, talc, and titanium dioxide.

Each TIVICAY PD tablet for oral suspension contains 5.26 mg of dolutegravir sodium, which is equivalent to 5 mg dolutegravir free acid, and the following inactive ingredients: calcium sulfate dihydrate, crospovidone, mannitol, microcrystalline cellulose, povidone K29/32, silicified microcrystalline cellulose, sodium starch glycolate, strawberry cream flavor, sucralose, and sodium stearyl fumarate. The tablet film-coating contains hypromellose, polyethylene glycol, and titanium dioxide.

12 CLINICAL PHARMACOLOGY

12.1 Mechanism of Action

Dolutegravir is an HIV-1 antiretroviral agent [see Microbiology (12.4)].

12.2 Pharmacodynamics

Effects on Electrocardiogram

In a randomized, placebo-controlled, cross-over trial, 42 healthy subjects received single-dose oral administrations of placebo, dolutegravir 250-mg suspension (exposures approximately 3–fold of the 50-mg once-daily dose at steady state), and moxifloxacin 400 mg (active control) in random sequence. After baseline and placebo adjustment, the maximum mean QTc change based on Fridericia correction method (QTcF) for dolutegravir was 2.4 msec (1-sided 95% upper CI: 4.9 msec). TIVICAY did not prolong the QTc interval over 24 hours postdose.

Effects on Renal Function

The effect of dolutegravir on renal function was evaluated in an open-label, randomized, 3‑arm, parallel, placebo-controlled trial in healthy subjects (n = 37) who received dolutegravir 50 mg once daily (n = 12), dolutegravir 50 mg twice daily (n = 13), or placebo once daily (n = 12) for 14 days. A decrease in creatinine clearance, as determined by 24-hour urine collection, was observed with both doses of dolutegravir after 14 days of treatment in subjects who received 50 mg once daily (9% decrease) and 50 mg twice daily (13% decrease). Neither dose of dolutegravir had a significant effect on the actual glomerular filtration rate (determined by the clearance of probe drug, iohexol) or effective renal plasma flow (determined by the clearance of probe drug, para-amino hippurate) compared with the placebo.

12.3 Pharmacokinetics

The pharmacokinetic properties of dolutegravir have been evaluated in healthy adult subjects and HIV‑1–infected adult subjects. Exposure to dolutegravir was generally similar between healthy subjects and HIV‑1–infected subjects. The non-linear exposure of dolutegravir following 50 mg twice daily compared with 50 mg once daily in HIV‑1–infected subjects (Table 9) was attributed to the use of metabolic inducers in the background antiretroviral regimens of subjects receiving dolutegravir 50 mg twice daily in clinical trials.

Table 9. Dolutegravir Steady-State Pharmacokinetic Parameter Estimates in HIV-1–Infected Adults
Parameter | 50 mg Once Daily; Geometric Meana(%CV) | 50 mg Twice Daily; Geometric Meanb(%CV)
AUC(0-24)(mcg ∙ h/mL) | 53.6 (27) | 75.1 (35)
Cmax(mcg/mL) | 3.67 (20) | 4.15 (29)
Cmin(mcg/mL) | 1.11 (46) | 2.12 (47)
a Based on population pharmacokinetic analyses using data from SPRING-1 and SPRING-2.
b Based on population pharmacokinetic analyses using data from VIKING (ING112961) and VIKING-3.

TIVICAY tablets and TIVICAY PD tablets for oral suspension are not bioequivalent. The relative bioavailability of TIVICAY PD is approximately 1.6-fold higher than TIVICAY; therefore, the 2 dosage forms are not substitutable on a milligram-per-milligram basis [see Dosage and Administration (2.3)].

Absorption

Following oral administration of dolutegravir, peak plasma concentrations were observed 1 to 3 hours postdose. With once-daily dosing, pharmacokinetic steady state is achieved within approximately 5 days with average accumulation ratios for AUC, Cmax, and C24 hranging from 1.2 to 1.5.

Dolutegravir plasma concentrations increased in a less than dose-proportional manner above 50 mg. Dolutegravir is a P‑gp substrate in vitro. The absolute bioavailability of dolutegravir has not been established.

Effect of Food:TIVICAY or TIVICAY PD may be taken with or without food. Food increased the extent of absorption and slowed the rate of absorption of dolutegravir following a 50-mg dose of TIVICAY. Low-, moderate-, and high-fat meals increased dolutegravir AUC(0-∞)by 33%, 41%, and 66%; increased Cmaxby 46%, 52%, and 67%; and prolonged Tmaxto 3, 4, and 5 hours from 2 hours under fasted conditions, respectively.

Distribution

Dolutegravir is highly bound (greater than or equal to 98.9%) to human plasma proteins based on in vivo data and binding is independent of plasma concentration of dolutegravir. The apparent volume of distribution (Vd/F) following 50-mg once-daily administration is estimated at 17.4 L based on a population pharmacokinetic analysis.

Cerebrospinal Fluid (CSF):In 12 treatment-naïve subjects on dolutegravir 50 mg daily plus abacavir/lamivudine, the median dolutegravir concentration in CSF was 13.2 ng/mL (range: 3.74 ng/mL to 18.3 ng/mL) 2 to 6 hours postdose after 16 weeks of treatment. The clinical relevance of this finding has not been established.

Elimination

Dolutegravir has a terminal half-life of approximately 14 hours and an apparent clearance (CL/F) of 1.0 L/h based on population pharmacokinetic analyses.

Metabolism:Dolutegravir is primarily metabolized via UGT1A1 with some contribution from CYP3A.

Polymorphisms in Drug‑ Metabolizing Enzymes:In a meta-analysis of healthy subject trials, subjects with UGT1A1 (n = 7) genotypes conferring poor dolutegravir metabolism had a 32% lower clearance of dolutegravir and 46% higher AUC compared with subjects with genotypes associated with normal metabolism via UGT1A1 (n = 41).

Excretion:After a single oral dose of [^14C] dolutegravir, 53% of the total oral dose was excreted unchanged in feces. Thirty-one percent of the total oral dose was excreted in urine, represented by an ether glucuronide of dolutegravir (18.9% of total dose), a metabolite formed by oxidation at the benzylic carbon (3.0% of total dose), and its hydrolytic N-dealkylation product (3.6% of total dose). Renal elimination of unchanged drug was low (less than 1% of the dose).

Specific Populations

Pediatric Patients:The pharmacokinetics of dolutegravir were evaluated in the IMPAACT P1093 trial and in 2 weight-band-based pharmacokinetic substudies from the ODYSSEY trial. Steady-state plasma exposure at doses by weight band are summarized in Table 10 [see Clinical Studies (14.3)] .

Mean dolutegravir AUC0-24hand C24hin HIV-1–infected pediatric subjects were comparable to those in adults after 50 mg once daily or 50 mg twice daily. Mean Cmaxis higher in pediatrics, but the increase is not considered clinically significant as the safety profiles were similar in pediatric and adult subjects [see Use in Specific Populations (8.4)] .

Table 10. Summary of Pharmacokinetic Parameters in Pediatric HIV-1–Infected Subjects (Pooled Analyses for IMPAACT P1093 and ODYSSEYaTrials)
Weight Band | Dosebof TIVICAY or TIVICAY PD | n | Pharmacokinetic Parameter Geometric Mean (%CV)
Weight Band | Dosebof TIVICAY or TIVICAY PD | n | Cmax (mcg/mL) | AUC0-24h (mcg∙h/mL) | C24h (ng/mL)
3 kg to <6 kg | TIVICAY PD 5 mg once daily | 8 | 3.80 (34) | 49.37 (49) | 962 (98)
6 kg to <10 kg | TIVICAY PD 15 mg once daily | 17 | 5.27 (50) | 57.17 (76) | 706 (177)
10 kg to <14 kg | TIVICAY PD 20 mg once daily | 13 | 5.99 (33) | 68.75 (48) | 977 (100)
14 kg to <20 kg | TIVICAY PD 25 mg once daily | 19 | 5.97 (42) | 58.97 (44) | 725 (75)
20 kg to <25 kg | TIVICAY PD 30 mg once daily | 9 | 7.16 (26) | 71.53 (26) | 759 (73)
≥20 kg | TIVICAY 50 mg once daily | 49 | 4.92 (40) | 54.98 (43) | 778 (62)
a Data from 2 weight-band-based pharmacokinetic substudies in the ODYSSEY trial.
b The bioavailability of TIVICAY PD tablets for oral suspension is ~1.6-fold that of TIVICAY tablets.

Geriatric Patients:Population pharmacokinetic analysis indicated age had no clinically relevant effect on the pharmacokinetics of dolutegravir.

Patients with Hepatic Impairment:In a trial comparing 8 subjects with moderate hepatic impairment (Child-Pugh Score B) with 8 matched healthy controls, exposure of dolutegravir from a single 50-mg dose was similar between the 2 groups. The effect of severe hepatic impairment (Child-Pugh Score C) on the pharmacokinetics of dolutegravir has not been studied.

Patients with Renal Impairment:In a trial evaluating the pharmacokinetics of a single 50-mg tablet of dolutegravir comparing 8 subjects with severe renal impairment (CrCl less than 30 mL/min) with 8 matched healthy controls, AUC, Cmax, and C24of dolutegravir were lower by 40%, 23%, and 43%, respectively, compared with those in matched healthy subjects. Population pharmacokinetic analysis using data from SAILING and VIKING-3 trials indicated that mild and moderate renal impairment had no clinically relevant effect on the exposure of dolutegravir. There is inadequate information to recommend appropriate dosing of dolutegravir in patients requiring dialysis.

HBV or HCV Co-infected Patients:Population analyses using pooled pharmacokinetic data from adult trials indicated no clinically relevant effect of HCV co-infection on the pharmacokinetics of dolutegravir. There were limited data on HBV co-infection.

Gender and Race:Population analyses using pooled pharmacokinetic data from adult trials indicated gender and race had no clinically relevant effect on the exposure of dolutegravir.

Drug Interaction Studies

Drug interaction trials were performed with TIVICAY and other drugs likely to be coadministered or commonly used as probes for pharmacokinetic interactions. The effects of dolutegravir on the exposure of coadministered drugs are summarized in Table 11and the effects of coadministered drugs on the exposure of dolutegravir are summarized in Table 12.

Dosing or regimen recommendations as a result of established and other potentially significant drug-drug interactions with TIVICAY are provided in Table 8 [see Dosage and Administration (2.2), Drug Interactions (7.3)] .

Table 11. Summary of Effect of Dolutegravir on the Pharmacokinetics of Coadministered Drugs
Coadministered Drug(s); and Dose(s) | Dose of TIVICAY | n | Geometric Mean Ratio (90% CI) of Pharmacokinetic Parameters of Coadministered Drug with/without Dolutegravir No Effect = 1.00
Coadministered Drug(s); and Dose(s) | Dose of TIVICAY | n | Cmax | AUC | Cτor C24
Elbasvir; 50 mg once daily | 50 mg; single dose | 12 | 0.97; (0.89, 1.05) | 0.98; (0.93, 1.04) | 0.98; (0.93, 1.03)
Ethinyl estradiol 0.035 mg | 50 mg twice daily | 15 | 0.99 (0.91 to 1.08) | 1.03 (0.96 to 1.11) | 1.02 (0.93 to 1.11)
Grazoprevir; 200 mg once daily | 50 mg; single dose | 12 | 0.64; (0.44, 0.93) | 0.81; (0.67, 0.97) | 0.86; (0.79, 0.93)
Metformin 500 mg twice daily | 50 mg once daily | 15a | 1.66 (1.53 to 1.81) | 1.79 (1.65 to 1.93) | _
Metformin 500 mg twice daily | 50 mg twice daily | 15a | 2.11 (1.91 to 2.33) | 2.45 (2.25 to 2.66) | _
Methadone 16 to 150 mg | 50 mg twice daily | 11 | 1.00 (0.94 to 1.06) | 0.98 (0.91 to 1.06) | 0.99 (0.91 to 1.07)
Midazolam 3 mg | 25 mg once daily | 10 | _ | 0.95 (0.79 to 1.15) | _
Norelgestromin 0.25 mg | 50 mg twice daily | 15 | 0.89 (0.82 to 0.97) | 0.98 (0.91 to 1.04) | 0.93 (0.85 to 1.03)
Rilpivirine 25 mg once daily | 50 mg once daily | 16 | 1.10 (0.99 to 1.22) | 1.06 (0.98 to 1.16) | 1.21 (1.07 to 1.38)
Sofosbuvir; 400 mg once daily; Metabolite (GS-331007) | 50 mg; once daily | 24 | 0.88; (0.80, 0.98) | 0.92; (0.85, 0.99) | NA
Sofosbuvir; 400 mg once daily; Metabolite (GS-331007) | 50 mg; once daily | 24 | 1.01; (0.93, 1.10) | 0.99; (0.97, 1.01) | 0.99; (0.97, 1.01)
Tenofovir disoproxil fumarate 300 mg once daily | 50 mg once daily | 15 | 1.09 (0.97 to 1.23) | 1.12 (1.01 to 1.24) | 1.19 (1.04 to 1.35)
Velpatasvir; 100 mg once daily | 50 mg; once daily | 24 | 0.94; (0.86, 1.02) | 0.91; (0.84, 0.98) | 0.88; (0.82, 0.94)
a The number of subjects represents the maximum number of subjects that were evaluated.

Table 12. Summary of Effect of Coadministered Drugs on the Pharmacokinetics of Dolutegravir
Coadministered Drug(s); and Dose(s) | Dose of TIVICAY | n | Geometric Mean Ratio (90% CI) of Dolutegravir Pharmacokinetic Parameters with/without Coadministered Drugs No Effect = 1.00
Coadministered Drug(s); and Dose(s) | Dose of TIVICAY | n | Cmax | AUC | Cτor C24
Atazanavir 400 mg once daily | 30 mg once daily | 12 | 1.50 (1.40 to 1.59) | 1.91 (1.80 to 2.03) | 2.80 (2.52 to 3.11)
Atazanavir/ritonavir 300/100 mg once daily | 30 mg once daily | 12 | 1.34 (1.25 to 1.42) | 1.62 (1.50 to 1.74) | 2.21 (1.97 to 2.47)
Darunavir/ritonavir 600/100 mg twice daily | 30 mg once daily | 15 | 0.89 (0.83 to 0.97) | 0.78 (0.72 to 0.85) | 0.62 (0.56 to 0.69)
Efavirenz 600 mg once daily | 50 mg once daily | 12 | 0.61 (0.51 to 0.73) | 0.43 (0.35 to 0.54) | 0.25 (0.18 to 0.34)
Elbasvir/grazoprevir; 50/200 mg once daily | 50 mg; single dose | 12 | 1.22; (1.05, 1.40) | 1.16; (1.00, 1.34) | 1.14; (0.95, 1.36)
Etravirine 200 mg twice daily | 50 mg once daily | 16 | 0.48 (0.43 to 0.54) | 0.29 (0.26 to 0.34) | 0.12 (0.09 to 0.16)
Etravirine + darunavir/ritonavir 200 mg + 600/100 mg twice daily | 50 mg once daily | 9 | 0.88 (0.78 to 1.00) | 0.75 (0.69 to 0.81) | 0.63 (0.52 to 0.76)
Etravirine + lopinavir/ritonavir 200 mg + 400/100 mg twice daily | 50 mg once daily | 8 | 1.07 (1.02 to 1.13) | 1.11 (1.02 to 1.20) | 1.28 (1.13 to 1.45)
Fosamprenavir/ritonavir 700 mg/100 mg twice daily | 50 mg once daily | 12 | 0.76 (0.63 to 0.92) | 0.65 (0.54 to 0.78) | 0.51 (0.41 to 0.63)
Lopinavir/ritonavir 400/100 mg twice daily | 30 mg once daily | 15 | 1.00 (0.94 to 1.07) | 0.97 (0.91 to 1.04) | 0.94 (0.85 to 1.05)
Rilpivirine 25 mg once daily | 50 mg once daily | 16 | 1.13 (1.06 to 1.21) | 1.12 (1.05 to 1.19) | 1.22 (1.15 to 1.30)
Tenofovir 300 mg once daily | 50 mg once daily | 15 | 0.97 (0.87 to 1.08) | 1.01 (0.91 to 1.11) | 0.92; (0.82 to 1.04)
Tipranavir/ritonavir 500/200 mg twice daily | 50 mg once daily | 14 | 0.54 (0.50 to 0.57) | 0.41 (0.38 to 0.44) | 0.24 (0.21 to 0.27)
Antacid (MAALOX) simultaneous administration | 50 mg single dose | 16 | 0.28 (0.23 to 0.33) | 0.26 (0.22 to 0.32) | 0.26 (0.21 to 0.31)
Antacid (MAALOX) 2 h after dolutegravir | 50 mg single dose | 16 | 0.82 (0.69 to 0.98) | 0.74 (0.62 to 0.90) | 0.70 (0.58 to 0.85)
Calcium carbonate 1,200 mg simultaneous administration (fasted) | 50 mg single dose | 12 | 0.63 (0.50 to 0.81) | 0.61 (0.47 to 0.80) | 0.61 (0.47 to 0.80)
Calcium carbonate 1,200 mg simultaneous administration (fed) | 50 mg single dose | 11 | 1.07 (0.83 to 1.38) | 1.09 (0.84 to 1.43) | 1.08 (0.81 to 1.42)
Calcium carbonate 1,200 mg 2 h after dolutegravir | 50 mg single dose | 11 | 1.00 (0.78 to 1.29) | 0.94 (0.72 to 1.23) | 0.90 (0.68 to 1.19)
Carbamazepine 300 mg twice daily | 50 mg once daily | 16a | 0.67 (0.61 to 0.73) | 0.51 (0.48 to 0.55) | 0.27 (0.24 to 0.31)
Ferrous fumarate 324 mg simultaneous administration (fasted) | 50 mg single dose | 11 | 0.43 (0.35 to 0.52) | 0.46 (0.38 to 0.56) | 0.44 (0.36 to 0.54)
Ferrous fumarate 324 mg simultaneous administration (fed) | 50 mg single dose | 11 | 1.03 (0.84 to 1.26) | 0.98 (0.81 to 1.20) | 1.00 (0.81 to 1.23)
Ferrous fumarate 324 mg 2 h after dolutegravir | 50 mg single dose | 10 | 0.99 (0.81 to 1.21) | 0.95 (0.77 to 1.15) | 0.92 (0.74 to 1.13)
Multivitamin (One-A-Day) simultaneous administration | 50 mg single dose | 16 | 0.65 (0.54 to 0.77) | 0.67 (0.55 to 0.81) | 0.68 (0.56 to 0.82)
Omeprazole 40 mg once daily | 50 mg single dose | 12 | 0.92 (0.75 to 1.11) | 0.97 (0.78 to 1.20) | 0.95 (0.75 to 1.21)
Prednisone 60 mg once daily with taper | 50 mg once daily | 12 | 1.06 (0.99 to 1.14) | 1.11 (1.03 to 1.20) | 1.17 (1.06 to 1.28)
Rifampinb 600 mg once daily | 50 mg twice daily | 11 | 0.57 (0.49 to 0.65) | 0.46 (0.38 to 0.55) | 0.28 (0.23 to 0.34)
Rifampinc 600 mg once daily | 50 mg twice daily | 11 | 1.18 (1.03 to 1.37) | 1.33 (1.15 to 1.53) | 1.22 (1.01 to 1.48)
Rifabutin 300 mg once daily | 50 mg once daily | 9 | 1.16 (0.98 to 1.37) | 0.95 (0.82 to 1.10) | 0.70 (0.57 to 0.87)
a The number of subjects represents the maximum number of subjects that were evaluated.
b Comparison is rifampin taken with dolutegravir 50 mg twice daily compared with dolutegravir 50 mg twice daily.
c Comparison is rifampin taken with dolutegravir 50 mg twice daily compared with dolutegravir 50 mg once daily.

12.4 Microbiology

Mechanism of Action

Dolutegravir inhibits HIV integrase by binding to the integrase active site and blocking the strand transfer step of retroviral DNA integration which is essential for the HIV replication cycle. Strand transfer biochemical assays using purified HIV-1 integrase and pre-processed substrate DNA resulted in IC50values of 2.7 nM and 12.6 nM.

Antiviral Activity in Cell Culture

Dolutegravir exhibited antiviral activity against laboratory strains of wild-type HIV-1 with mean EC50values of 0.5 nM (0.21 ng/mL) to 2.1 nM (0.85 ng/mL) in peripheral blood mononuclear cells (PBMCs) and MT-4 cells. Dolutegravir exhibited antiviral activity against 13 clinically diverse clade B isolates with a mean EC50value of 0.52 nM in a viral integrase susceptibility assay using the integrase coding region from clinical isolates. Dolutegravir demonstrated antiviral activity in cell culture against a panel of HIV-1 clinical isolates (3 in each group of M clades A, B, C, D, E, F, and G, and 3 in group O) with EC50values ranging from 0.02 nM to 2.14 nM for HIV-1. Dolutegravir EC50values against 3 HIV-2 clinical isolates in PBMC assays ranged from 0.09 nM to 0.61 nM.

Antiviral Activity in Combination with Other Antiviral Agents

The antiviral activity of dolutegravir was not antagonistic when combined with the INSTI, raltegravir; non-nucleoside reverse transcriptase inhibitors (NNRTIs), efavirenz or nevirapine; the NRTIs, abacavir or stavudine; the protease inhibitors (PIs), amprenavir or lopinavir; the CCR5 co-receptor antagonist, maraviroc; or the fusion inhibitor, enfuvirtide. Dolutegravir antiviral activity was not antagonistic when combined with the HBV reverse transcriptase inhibitor, adefovir, or inhibited by the antiviral, ribavirin.

Resistance

Cell Culture:Dolutegravir-resistant viruses were selected in cell culture starting from different wild-type HIV-1 strains and clades. Amino acid substitutions E92Q, G118R, S153F or Y, G193E or R263K emerged in different passages and conferred decreased susceptibility to dolutegravir of up to 4-fold. Passage of mutant viruses containing the Q148R or Q148H substitutions selected for additional substitutions in integrase that conferred decreased susceptibility to dolutegravir (fold-change increase of 13 to 46). The additional integrase substitutions included T97A, E138K, G140S, and M154I. Passage of mutant viruses containing both G140S and Q148H selected for L74M, E92Q, and N155H.

Treatment-Naïve Subjects:No subject who received dolutegravir 50-mg once-daily in the treatment-naïve trials SPRING-2 (96 weeks) and SINGLE (144 weeks) had a detectable decrease in susceptibility to dolutegravir or background NRTIs in the resistance analysis subset (n = 12 with HIV-1 RNA greater than 400 copies per mL at failure or last visit and having resistance data). Two virologic failure subjects in SINGLE had treatment-emergent G/D/E193D and G193G/E integrase substitutions at Week 84 and Week 108, respectively, and 1 subject with 275 copies/mLHIV-1 RNA had a treatment-emergent Q157Q/P integrase substitution detected at Week 24. None of these subjects had a corresponding decrease in dolutegravir susceptibility. No treatment-emergent genotypic resistance to the background regimen was observed in the dolutegravir arm in either the SPRING-2 or SINGLE trials. No treatment-emergent primary resistance substitutions were observed in either treatment group in the FLAMINGO trial through Week 96.

Treatment-Experienced, Integrase Strand Transfer Inhibitor-Naïve Subjects:In the dolutegravir arm of the SAILING trial for treatment-experienced and INSTI-naïve subjects (n = 354), treatment-emergent integrase substitutions were observed in 6 of 28 (21%) subjects who had virologic failure and resistance data. In 5 of the 6 subjects’ isolates emergent INSTI substitutions included L74L/M/I, Q95Q/L, V151V/I (n = 1 each), and R263K (n = 2). The change in dolutegravir phenotypic susceptibility for these 5 subject isolates was less than 2-fold. One subject isolate had pre-existing raltegravir resistance substitutions E138A, G140S, and Q148H at baseline and had additional emergent INSTI-resistance substitutions T97A and E138A/T with a corresponding 148-fold reduction in dolutegravir susceptibility at failure. In the comparator raltegravir arm, 21 of 49 (43%) subjects with post-baseline resistance data had evidence of emergent INSTI-resistance substitutions (L74M, E92Q, T97A, E138Q, G140S/A, Y143R/C, Q148H/R, V151I, N155H, E157Q, and G163K/R) and raltegravir phenotypic resistance.

Virologically Suppressed Subjects:SWORD-1 and SWORD-2 are identical trials in virologically suppressed subjects receiving 2 NRTIs plus either an INSTI, an NNRTI, or a PI, that switched to dolutegravir plus rilpivirine (n = 513) or remained on their current antiviral regimen (n = 511). In the pooled SWORD-1 and SWORD-2 trials, 12 subjects (7 in SWORD-1 and 5 in SWORD-2) had confirmed virologic failure (HIV-1 RNA greater than 200 copies/mL) while receiving dolutegravir plus rilpivirine at any time through Week 148. Ten of the confirmed virologic failures had post-baseline resistance data, with 6 isolates showing evidence of rilpivirine resistance, and 2 with evidence of dolutegravir resistance substitutions. Six isolates showed genotypic and/or phenotypic resistance to rilpivirine with emergent NNRTI-resistance substitutions E138E/A (rilpivirine 1.6-fold change), M230M/L (rilpivirine 2-fold change), L100L/I, K101Q, and E138A (rilpivirine 4.1-fold change), K101K/E (rilpivirine 1.2-fold change), K101K/E, M230M/L (rilpivirine 2-fold change), and L100L/V/M, M230M/L (rilpivirine 31-fold change). In addition, 1 virologic failure subject had NNRTI‑resistance substitutions K103N and V179I at Week 88 with rilpivirine phenotypic fold change of 5.2 but had no baseline sample.

One virologic failure isolate had emergent INSTI‑resistance substitution V151V/I present post-baseline with baseline INSTI‑resistance substitutions N155N/H and G163G/R (by exploratory HIV proviral DNA archive sequencing); no integrase phenotypic data were available for this isolate at virologic failure. One other subject had the dolutegravir resistance substitution G193E at baseline and virologic failure, but no detectable phenotypic resistance (fold change = 1.02) at Week 24.

No resistance-associated substitutions were observed for the 2 subjects meeting confirmed virologic failure in the comparative current antiretroviral regimen arms at Week 48.

Treatment-Experienced, Integrase Strand Transfer Inhibitor-Experienced Subjects:VIKING-3 examined the efficacy of dolutegravir 50 mg twice daily plus optimized background therapy in subjects with prior or current virologic failure on an INSTI- (elvitegravir or raltegravir) containing regimen. Use of TIVICAY in INSTI-experienced patients should be guided by the number and type of baseline INSTI substitutions. The efficacy of TIVICAY 50 mg twice daily is reduced in patients with an INSTI-resistance Q148 substitution plus 2 or more additional INSTI-resistance substitutions, including T66A, L74I/M, E138A/K/T, G140S/A/C, Y143R/C/H, E157Q, G163S/E/K/Q, or G193E/R.

Response by Baseline Genotype

Of the 183 subjects with baseline data, 30% harbored virus with a substitution at Q148, and 33% had no primary INSTI-resistance substitutions (T66A/I/K, E92Q/V, Y143R/C/H, Q148H/R/K, and N155H) at baseline, but had historical genotypic evidence of INST-resistance substitutions, phenotypic evidence of elvitegravir or raltegravir resistance, or genotypic evidence of INSTI-resistance substitutions at screening.

Response rates by baseline genotype were analyzed in an “as-treated” analysis at Week 48 (n = 175) (Table 13). The response rate at Week 48 to dolutegravir-containing regimens was 47% (24 of 51) when Q148 substitutions were present at baseline; Q148 was always present with additional INSTI-resistance substitutions (Table 13). In addition, a diminished virologic response of 40% (6 of 15) was observed when the substitution E157Q or K was present at baseline with other INSTI-resistance substitutions but without a Q148H or R substitution.

Table 13. Response by Baseline Integrase Genotype in Subjects with Prior Experience to an Integrase Strand Transfer Inhibitor in VIKING-3
Baseline Genotype | Week 48 (<50 copies/mL) n = 175
Overall Response | 66% (116/175)
No Q148 substitutiona | 74% (92/124)
Q148H/R + G140S/A/C without additional INSTI-resistance substitutionb | 61% (17/28)
Q148H/R + ≥2 INSTI-resistance substitutionsb,c | 29% (6/21)
INSTI = integrase strand transfer inhibitor.
a Includes INSTI-resistance substitutions Y143R/C/H and N155H.
b INSTI-resistance substitutions included T66A, L74I/M, E138A/K/T, G140S/A/C, Y143R/C/H, E157Q, G163S/E/K/Q, or G193E/R. Two additional subjects had baseline genotypes of Q148Q/R plus L74L/I/M (virologic failure) and Q148R plus E138K (responder).
c The most common pathway with Q148H/R + greater than or equal to 2 INSTI-resistance substitutions had Q148+G140+E138 substitutions (n = 16).

Response by Baseline Phenotype

Response rates by baseline phenotype were analyzed in an as-treated analysis using all subjects with available baseline phenotypes through Week 48 (n = 163) (Table 14). These baseline phenotypic groups are based on subjects enrolled in VIKING-3 and are not meant to represent definitive clinical susceptibility cut points for dolutegravir. The data are provided to guide clinicians on the likelihood of virologic success based on pretreatment susceptibility to dolutegravir in INSTI-resistant patients.

Table 14. Response by Baseline Dolutegravir Phenotype (Fold-Change from Reference) in Subjects with Prior Experience to an Integrase Strand Transfer Inhibitor in VIKING-3
Baseline Dolutegravir Phenotype (Fold-Change from Reference) | Response at Week 48 (<50 copies/mL) Subset n = 163
Overall Response | 64% (104/163)
<3-fold change | 72% (83/116)
3- <10-fold change | 53% (18/34)
≥10-fold change | 23% (3/13)

Integrase Strand Transfer Inhibitor Treatment-Emergent Resistance

There were 50 subjects with virologic failure on the dolutegravir twice-daily regimen in VIKING-3 with HIV-1 RNA greater than 400 copies/mL at the failure timepoint, Week 48 or beyond, or the last timepoint on trial. Thirty-nine subjects with virologic failure had resistance data that were used in the Week 48 analysis. In the Week 48 resistance analysis 85% (33 of 39) of the subjects with virologic failure had treatment-emergent INSTI-resistance substitutions in their isolates. The most common treatment-emergent INSTI-resistance substitution was T97A. Other frequently emergent INSTI-resistance substitutions included L74M, I or V, E138K or A, G140S, Q148H, R or K, M154I, or N155H. Substitutions E92Q, Y143R or C/H, S147G, V151A, and E157E/Q each emerged in 1 to 3 subjects’ isolates. At failure, the median dolutegravir fold-change from reference was 61-fold (range: 0.75 to 209) for isolates with emergent INSTI-resistance substitutions (n = 33).

Resistance to one or more background drugs in the dolutegravir twice-daily regimen also emerged in 49% (19 of 39) of subjects in the Week 48 resistance analysis .

In VIKING-4 (ING116529), 30 subjects with current virological failure on an INSTI-containing regimen and genotypic evidence of INSTI-resistance substitutions at screening were randomized to receive either dolutegravir 50 mg twice daily or placebo with the current failing regimen for 7 days and then all subjects received open-label dolutegravir plus optimized background regimen from Day 8. Virologic responses at Week 48 by baseline genotypic and phenotypic INSTI-resistance categories and the INSTI resistance-associated substitutions that emerged on dolutegravir treatment in VIKING-4 were consistent with those seen in VIKING-3.

Cross-Resistance

Site-Directed Integrase Strand Transfer Inhibitor-Resistant Mutant HIV-1 and HIV-2 Strains:The susceptibility of dolutegravir was tested against 60 INSTI-resistant site-directed mutant HIV-1 viruses (28 with single substitutions and 32 with 2 or more substitutions) and 6 INSTI-resistant site-directed mutant HIV-2 viruses. The single INSTI-resistance substitutions T66K, I151L, and S153Y conferred a greater than 2-fold decrease in dolutegravir susceptibility (range: 2.3-fold to 3.6-fold from reference). Combinations of multiple substitutions T66K/L74M, E92Q/N155H, G140C/Q148R, G140S/Q148H, R or K, Q148R/N155H, T97A/G140S/Q148, and substitutions at E138/G140/Q148 showed a greater than 2-fold decrease in dolutegravir susceptibility (range: 2.5-fold to 21-fold from reference). In HIV-2 mutants, combinations of substitutions A153G/N155H/S163G and E92Q/T97A/N155H/S163D conferred 4-fold decreases in dolutegravir susceptibility, and E92Q/N155H and G140S/Q148R showed 8.5-fold and 17-fold decreases in dolutegravir susceptibility, respectively.

Reverse Transcriptase Inhibitor- and Protease Inhibitor-Resistant Strains:Dolutegravir demonstrated equivalent antiviral activity against 2 NNRTI-resistant, 3 NRTI-resistant, and 2 PI-resistant HIV-1 mutant clones compared with the wild-type strain.

13 NONCLINICAL TOXICOLOGY

13.1 Carcinogenesis, Mutagenesis, Impairment of Fertility

Carcinogenesis

Two-year carcinogenicity studies in mice and rats were conducted with dolutegravir. Mice were administered doses of up to 500 mg/kg, and rats were administered doses of up to 50 mg/kg. In mice, no significant increases in the incidence of drug-related neoplasms were observed at the highest doses tested, resulting in dolutegravir AUC exposures approximately 14 times higher than those in humans at the maximum recommended dose. In rats, no increases in the incidence of drug-related neoplasms were observed at the highest dose tested, resulting in dolutegravir AUC exposures 10 times and 15 times higher in males and females, respectively, than those in humans at the maximum recommended dose.

Mutagenesis

Dolutegravir was not genotoxic in the bacterial reverse mutation assay, mouse lymphoma assay, or in the in vivo rodent micronucleus assay.

Impairment of Fertility

In a study conducted in rats, there were no effects on mating or fertility with dolutegravir up to 1,000 mg/kg/day. This dose is associated with an exposure that is approximately 24 times higher than the exposure in humans at the maximum recommended dose.

14 CLINICAL STUDIES

14.1 Description of Clinical Studies

The efficacy and safety of TIVICAY or TIVICAY PD were evaluated in the studies summarized in Table 15.

Table 15. Trials Conducted with TIVICAY or TIVICAY PD in HIV-1–Infected Subjects
Population | Trial | Trial Arms | Timepoint (Week)
Adults:
- Treatment-naïve | SPRING-2 (ING113086) (NCT01227824) | TIVICAY + 2 NRTIs (n = 403); Raltegravir + 2 NRTIs (n = 405) | 96
- Treatment-naïve | SINGLE (ING114467) (NCT01263015) | TIVICAY + EPZICOM (n = 414); ATRIPLA (n = 419) | 144
- Treatment-naïve | FLAMINGO (ING114915) (NCT01449929) | TIVICAY + NRTI BR (n = 243); Darunavir/ritonavir + NRTI BR (n = 242) | 96
- Treatment-experienced, INSTI-naïve | SAILING (ING111762) (NCT01231516) | TIVICAY + BR (n = 354); Raltegravir + BR (n = 361) | 48
- INSTI-experienced | VIKING-3 (ING112574); (NCT01328041) | TIVICAY + OBT (n = 183) | 48
- Virologically suppressed | SWORD-1 (NCT02429791); SWORD-2 (NCT02422797) | Pooled presentation; TIVICAY + Rilpivirine (n = 513); CAR (n = 511) | 48
Pediatrics:; - 4 weeks and older and weighing at least 3 kg without INSTI resistance | IMPAACT P1093 (NCT01302847) | TIVICAY or TIVICAY PD + BR (n = 75) | 24
NRTI = nucleoside reverse transcriptase inhibitor; BR = Background regimen; INSTI = integrase strand transfer inhibitor; OBT = Optimized background therapy; CAR = Current antiretroviral regimen.

14.2 Adult Subjects

Treatment-Naïve Subjects

In SPRING-2, 822 subjects were randomized and received at least 1 dose of either TIVICAY 50 mg once daily or raltegravir 400 mg twice daily, both in combination with fixed-dose dual NRTI treatment (either abacavir sulfate and lamivudine [EPZICOM] or emtricitabine/tenofovir [TRUVADA]). There were 808 subjects included in the efficacy and safety analyses. At baseline, the median age of subjects was 36 years, 13% female, 15% non-white, 11% had hepatitis B and/or C virus co-infection, 2% were CDC Class C (AIDS), 28% had HIV-1 RNA greater than 100,000 copies per mL, 48% had CD4+ cell count less than 350 cells/mm^3, and 39% received EPZICOM; these characteristics were similar between treatment groups.

In SINGLE, 833 subjects were randomized and received at least 1 dose of either TIVICAY 50 mg once daily with fixed-dose abacavir sulfate and lamivudine (EPZICOM) or fixed-dose efavirenz/emtricitabine/tenofovir (ATRIPLA). At baseline, the median age of subjects was 35 years, 16% female, 32% non-white, 7% had hepatitis C co-infection (hepatitis B virus co-infection was excluded), 4% were CDC Class C (AIDS), 32% had HIV-1 RNA greater than 100,000 copies/mL, and 53% had CD4+ cell count less than 350 cells/mm^3; these characteristics were similar between treatment groups.

Outcomes for SPRING-2 (Week 96 analysis) and SINGLE (Week 144 open-label phase analysis which followed the Week 96 double-blind phase) are provided in Table 16. Side-by-side tabulation is to simplify presentation; direct comparisons across trials should not be made due to differing trial designs.

Table 16. Virologic Outcomes of Randomized Treatment in SPRING-2 at Week 96 and SINGLE at Week 144 (Snapshot Algorithm)
 | SPRING-2 Week 96 |  | SINGLE Week 144
 | TIVICAY 50 mg Once Daily + 2 NRTIs (n = 403) | Raltegravir 400 mg Twice Daily + 2 NRTIs (n = 405) | TIVICAY 50 mg + EPZICOM Once Daily (n = 414) | ATRIPLA Once Daily (n = 419)
HIV-1 RNA <50 copies/mL | 82% | 78% | 71% | 63%
Treatment differencea | 4.9% (95% CI: -0.6%, 10.3%)b |  | 8.3% (95% CI: 2.0%, 14.6%)c
Virologic nonresponse | 5% | 10% | 10% | 7%
Data in window not <50 copies/mL | 1% | 3% | 4% | <1%
Discontinued for lack of efficacy | 2% | 3% | 3% | 3%
Discontinued for other reasons while not suppressed | <1% | 3% | 3% | 4%
Change in ART regimen | <1% | <1% | 0 | 0
No virologic data | 12% | 12% | 18% | 30%
Reasons
Discontinued study/study drug due to adverse event or deathd | 2% | 2% | 4% | 14%
Discontinued study/study drug for other reasonse | 8% | 9% | 12% | 13%
Missing data during window but on study | 2% | <1% | 2% | 3%
Proportion (%) of Subjects with HIV-1 RNA <50 copies/mL by Baseline Category
Plasma viral load (copies/mL)
≤100,000 | 84% | 83% | 73% | 64%
>100,000 | 79% | 63% | 69% | 61%
Gender
Male | 84% | 79% | 72% | 66%
Female | 70% | 68% | 69% | 48%
Race
White | 83% | 78% | 72% | 71%
African-American/African Heritage/Other | 77% | 75% | 71% | 47%
NRTI = Nucleoside reverse transcriptase inhibitor.
a Adjusted for pre-specified stratification factors.
b The primary endpoint was assessed at Week 48 and the virologic success rate was 88% in the group receiving TIVICAY and 86% in the raltegravir group, with a treatment difference of 2.6% and 95% CI of (-1.9%, 7.2%).
c The primary endpoint was assessed at Week 48 and the virologic success rate was 88% in the group receiving TIVICAY and 81% in the ATRIPLA group, with a treatment difference of 7.4% and 95% CI of (2.5%, 12.3%).
d Includes subjects who discontinued due to an adverse event or death at any time point if this resulted in no virologic data on treatment during the analysis window.
e Other includes reasons such as withdrew consent, loss to follow-up, moved, and protocol deviation.

SPRING-2:Virologic outcomes were also comparable across baseline characteristics including CD4+ cell count, age, and use of EPZICOM or TRUVADA as NRTI background regimen. The median change in CD4+ cell counts from baseline was 276 cells/mm^3in the group receiving TIVICAY and 264 cells/mm^3for the raltegravir group at 96 weeks.

There was no treatment-emergent resistance to dolutegravir or to the NRTI background.

SINGLE:Treatment differences were maintained across baseline characteristics including baseline viral load, CD4+ cell count, age, gender, and race.

The adjusted mean changes in CD4+ cell counts from baseline were 378 cells/mm^3in the group receiving TIVICAY + EPZICOM and 332 cells/mm^3for the ATRIPLA group at 144 weeks. The adjusted difference between treatment arms and 95% CI was 46.9 cells/mm^3(15.6 cells/mm^3, 78.2 cells/mm^3) (adjusted for pre-specified stratification factors: baseline HIV-1 RNA, and baseline CD4+ cell count).

There was no treatment-emergent resistance to dolutegravir, abacavir, or lamivudine.

FLAMINGO:In FLAMINGO, 485 subjects were randomized and received at least 1 dose of either TIVICAY 50 mg once daily (n = 243) or darunavir + ritonavir 800 mg/100 mg once daily (n = 242), both in combination with investigator-selected NRTI background regimen (either fixed-dose abacavir and lamivudine [EPZICOM] or fixed-dose emtricitabine/tenofovir disoproxil fumarate [TRUVADA]). There were 484 subjects included in the efficacy and safety analyses. At baseline, the median age of subjects was 34 years, 15% female, 28% non-white, 10% had hepatitis B and/or C virus co-infection, 3% were CDC Class C (AIDS), 25% had HIV‑1 RNA greater than 100,000 copies/mL, and 35% had CD4+ cell count less than 350 cells/mm^3; these characteristics were similar between treatment groups. Overall response rates by Snapshot algorithm through Week 96 were 80% for TIVICAY and 68% for darunavir/ritonavir. The proportion of subjects who were non-responders (HIV-1 RNA greater than or equal to 50 copies per mL) at Week 96 was 8% and 12% in the arms receiving TIVICAY and darunavir + ritonavir, respectively; no virologic data were available for 12% and 21% for subjects treated with TIVICAY and darunavir + ritonavir, respectively. The adjusted overall response rate difference in proportion and 95% CI was 12.4% (4.7%, 20.2%). No treatment-emergent primary resistance substitutions were observed in either treatment group.

Treatment-Experienced, Integrase Strand Transfer Inhibitor-Naïve Subjects

In the international, multicenter, double-blind trial (SAILING), 719 HIV‑1–infected, antiretroviral treatment-experienced adults were randomized and received either TIVICAY 50 mg once daily or raltegravir 400 mg twice daily with investigator-selected background regimen consisting of up to 2 agents, including at least 1 fully active agent. There were 715 subjects included in the efficacy and safety analyses. At baseline, the median age was 43 years, 32% were female, 50% non-white, 16% had hepatitis B and/or C virus co-infection, 46% were CDC Class C (AIDS), 20% had HIV-1 RNA greater than 100,000 copies/mL, and 72% had CD4+ cell count less than 350 cells/mm^3; these characteristics were similar between treatment groups. All subjects had at least 2-class antiretroviral treatment resistance, and 49% of subjects had at least 3-class antiretroviral treatment resistance at baseline. Week 48 outcomes for SAILING are shown in Table 17.

Table 17. Virologic Outcomes of Randomized Treatment in SAILING at 48 Weeks (Snapshot Algorithm)
 | TIVICAY 50 mg Once Daily + BRa; (n = 354) | Raltegravir 400 mg Twice Daily + BRa; (n = 361)
HIV-1 RNA <50 copies/mL | 71% | 64%
Adjustedbtreatment difference | 7.4% (95% CI: 0.7%, 14.2%)
Virologic nonresponse | 20% | 28%
No virologic data | 9% | 9%
Reasons
Discontinued study/study drug due to adverse event or death | 3% | 4%
Discontinued study/study drug for other reasonsc | 5% | 4%
Missing data during window but on study | 2% | 1%
Proportion (%) with HIV-1 RNA <50 copies/mL by Baseline Category
Plasma viral load (copies/mL)
≤50,000 copies/mL | 75% | 71%
>50,000 copies/mL | 62% | 47%
Background regimen
No darunavir use | 67% | 60%
Darunavir use with primary PI substitutions | 85% | 67%
Darunavir use without primary PI substitutions | 69% | 70%
Gender
Male | 70% | 66%
Female | 74% | 60%
Race
White | 75% | 71%
African-American/African Heritage/Other | 67% | 57%
a BR = Background regimen. Background regimen was restricted to less than or equal to 2 antiretroviral treatments with at least 1 fully active agent.
b Adjusted for pre-specified stratification factors.
c Other includes reasons such as withdrew consent, loss to follow-up, moved, and protocol deviation.

Treatment differences were maintained across the baseline characteristics including CD4+ cell count and age.

The mean changes in CD4+ cell counts from baseline were 162 cells/mm^3in the group receiving TIVICAY and 153 cells/mm^3in the raltegravir group.

Treatment-Experienced, Integrase Strand Transfer Inhibitor-Experienced Subjects

VIKING-3 examined the effect of TIVICAY 50 mg twice daily over 7 days of functional monotherapy, followed by OBT with continued treatment of TIVICAY 50 mg twice daily.

In the multicenter, open-label, single-arm VIKING-3 trial, 183 HIV‑1–infected, antiretroviral treatment-experienced adults with virological failure and current or historical evidence of raltegravir and/or elvitegravir resistance received TIVICAY 50 mg twice daily with the current failing background regimen for 7 days, then received TIVICAY with OBT from Day 8. A total of 183 subjects enrolled: 133 subjects with INSTI resistance at screening and 50 subjects with only historical evidence of resistance (and not at screening). At baseline, median age of subjects was 48 years; 23% were female, 29% non-white, and 20% had hepatitis B and/or C virus co-infection. Median baseline CD4+ cell count was 140 cells/mm^3, median duration of prior antiretroviral treatment was 13 years, and 56% were CDC Class C. Subjects showed multiple-class antiretroviral treatment resistance at baseline: 79% had greater than or equal to 2 NRTI, 75% greater than or equal to 1 NNRTI, and 71% greater than or equal to 2 PI major substitutions; 62% had non-R5 virus.

Mean reduction from baseline in HIV-1 RNA at Day 8 (primary endpoint) was 1.4 log10(95% CI: 1.3 log10, 1.5 log10). Response at Week 48 was affected by baseline INSTI substitutions [see Microbiology (12.4)] .

After the functional monotherapy phase, subjects had the opportunity to re-optimize their background regimen when possible. Week 48 virologic outcomes for VIKING-3 are shown in Table 18.

Table 18. Virologic Outcomes of Treatment of VIKING-3 at 48 Weeks (Snapshot Algorithm)
 | TIVICAY 50 mg Twice Daily + OBT; (n = 183)
HIV-1 RNA <50 copies/mL | 63%
Virologic nonresponse | 32%
No virologic data; Reasons
Discontinued study/study drug due to adverse event or death | 3%
Proportion (%) with HIV-1 RNA <50 copies/mL by Baseline Category
Gender
Male | 63%
Female | 64%
Race
White | 63%
African-American/African Heritage/Other | 64%
OBT = Optimized Background Therapy.

Subjects harboring virus with Q148 and with additional Q148-associated secondary substitutions also had a reduced response at Week 48 in a stepwise fashion [see Microbiology (12.4)].

The median change in CD4+ cell count from baseline was 80 cells/mm^3at Week 48.

Virologically Suppressed Subjects

SWORD-1 and SWORD-2 are identical 148-week, Phase III, randomized, multicenter, parallel-group, non-inferiority trials. A total of 1,024 adult HIV-1–infected subjects who were on a stable suppressive antiretroviral regimen (containing 2 NRTIs plus either an INSTI, an NNRTI, or a PI) for at least 6 months (HIV-1 RNA less than 50 copies/mL), with no history of treatment failure and no known substitutions associated with resistance to dolutegravir or rilpivirine received treatment in the trials. Subjects were randomized 1:1 to continue their current antiretroviral regimen (n = 511) or be switched to TIVICAY 50 mg plus rilpivirine 25 mg administered once daily (n = 513). Subjects originally assigned to continue their current antiretroviral regimen and who remained virologically suppressed at Week 48 switched to TIVICAY plus rilpivirine at Week 52 (n = 477).

The primary efficacy endpoint for the SWORD trial was the proportion of subjects with plasma HIV-1 RNA less than 50 copies/mL at Week 48. The proportion of subjects with HIV-1 RNA less than 50 copies/mL at Week 48 was 95% for both treatment groups; treatment difference and 95% CI was -0.2% (-3.0%, 2.5%). The proportion of subjects with HIV‑1 RNA greater than or equal to 50 copies/mL (virologic failure) at Week 48 was 0.6% and 1.2% for the dolutegravir plus rilpivirine treatment group and the current antiretroviral regimen treatment groups, respectively; treatment difference and 95% CI was -0.6% (-1.7%, 0.6%). At Week 148 in the pooled SWORD-1 and SWORD-2 trials, 84% of subjects who received TIVICAY plus rilpivirine from study start had plasma HIV-1 RNA less than 50 copies/mL (Snapshot algorithm). In subjects who initially remained on their current antiretroviral regimen and switched to TIVICAY plus rilpivirine at Week 52, 90% had plasma HIV-1 RNA less than 50 copies/mL at Week 148 (Snapshot algorithm), which was comparable to the response rate (89%) observed at Week 100 (similar exposure duration) in subjects receiving TIVICAY plus rilpivirine from study start.

Refer to the prescribing information for JULUCA (dolutegravir and rilpivirine) tablet for complete virologic outcome information.

14.3 Pediatric Subjects

IMPAACT P1093 is an ongoing Phase I/II, multicenter, open-label trial to evaluate the pharmacokinetic parameters, safety, tolerability, and efficacy of TIVICAY or TIVICAY PD in combination treatment regimens in HIV-1–infected infants, children, and adolescents aged at least 4 weeks to 18 years. Subjects were stratified by 5 age cohorts: Cohort 1, aged 12 to less than 18 years; Cohort 2A, aged 6 to less than 12 years; Cohort 3, aged 2 to less than 6 years; Cohort 4, aged 6 months to less than 2 years; and Cohort 5, aged 4 weeks to less than 6 months. Seventy-five subjects received the recommended dose (determined by weight and age) of TIVICAY or TIVICAY PD [see Dosage and Administration (2.2, 2.3, 2.4)] .

These 75 subjects had a median age of 27 months (range: 1 to 214), were 59% female, and 68% were Black or African American. At baseline, mean plasma HIV-1 RNA was 4.4 log10 copies/mL, median CD4+ cell count was 1,225 cells/mm^3(range: 1 to 8,255), and median CD4+% was 23% (range: 0.3% to 49%). Overall, 33% had baseline plasma HIV-1 RNA greater than 50,000 copies/mL and 12% had a CDC HIV clinical classification of category C. The majority (80%) of subjects were treatment-experienced, but all were INSTI-naïve. Most subjects had previously used at least 1 NNRTI (44%) or 1 PI (76%).

Virologic outcomes from IMPAACT P1093 include subjects who received either TIVICAY tablets or TIVICAY PD tablets for oral suspension as per the dosing recommendations for their weight band and who had reached Week 24 (n = 58) or Week 48 (n = 42). At Week 24, 62% of subjects achieved HIV-1 RNA less than 50 copies/mL and 86% achieved HIV-1 RNA less than 400 copies/mL (Snapshot algorithm). The median CD4 count (percent) increase from baseline to Week 24 was 105 cells/mm^3(5%). At Week 48, 69% of subjects achieved HIV-1 RNA less than 50 copies/mL and 79% achieved HIV-1 RNA less than 400 copies/mL (Snapshot algorithm). The median CD4 count (percent) increase from baseline to Week 48 was 141 cells/mm^3(7%).

16 HOW SUPPLIED/STORAGE AND HANDLING

TIVICAY tablets, 50 mg, are yellow, round, film-coated, biconvex tablets debossed with “SV 572” on one side and “50” on the other side. Bottle of 30 tablets with child-resistant closure.

NDC 60760-748-07 BOTTLES OF 7

Store TIVICAY tablets at 25°C (77°F); excursions permitted 15° to 30°C (59° to 86°F) [See USP Controlled Room Temperature].

17 PATIENT COUNSELING INFORMATION

Advise the patient to read the FDA-approved patient labeling (Patient Information and Instructions for Use).

Drug Interactions

TIVICAY or TIVICAY PD may interact with other drugs; therefore, advise patients to report to their healthcare provider the use of any other prescription or nonprescription medication or herbal products, including St. John’s wort [see Contraindications (4), Warnings and Precautions (5.4), Drug Interactions (7)] .

Hypersensitivity Reactions

Advise patients to immediately contact their healthcare provider if they develop rash. Instruct patients to immediately stop taking TIVICAY or TIVICAY PD and other suspect agents, and seek medical attention if they develop a rash associated with any of the following symptoms, as it may be a sign of a more serious reaction such as severe hypersensitivity: fever; generally ill feeling; extreme tiredness; muscle or joint aches; blisters or peeling of the skin; oral blisters or lesions; eye inflammation; facial swelling; swelling of the eyes, lips, tongue, or mouth; breathing difficulty; and/or signs and symptoms of liver problems (e.g., yellowing of the skin or whites of the eyes, dark or tea-colored urine, pale-colored stools or bowel movements, nausea, vomiting, loss of appetite, or pain, aching, or sensitivity on the right side below the ribs) [see Warnings and Precautions (5.1)] .

Hepatotoxicity

Inform patients that hepatotoxicity has been reported with dolutegravir [see Warnings and Precautions (5.2)] . Advise patients that laboratory monitoring for hepatoxicity during therapy with TIVICAY or TIVICAY PD is recommended, especially for patients with liver disease, such as hepatitis B or C.

Immune Reconstitution Syndrome

Advise patients to inform their healthcare provider immediately of any signs or symptoms of infection as inflammation from previous infection may occur soon after combination antiretroviral therapy, including when TIVICAY or TIVICAY PD is started [see Warnings and Precautions (5.4)] .

Different Formulations Are Not Bioequivalent

Advise patients that TIVICAY and TIVICAY PD are not bioequivalent and are not substitutable on a milligram-per-milligram basis. Advise patients or their care provider that patients switching from one formulation to the other must adjust the dose for the new dosage formulation [see Dosage and Administration (2.2) and Warnings and Precautions (5.5)].

Pregnancy Registry

Inform patients that there is an antiretroviral pregnancy registry to monitor fetal outcomes in those exposed to TIVICAY or TIVICAY PD during pregnancy [see Use in Specific Populations (8.1)] .

Lactation

Inform individuals with HIV-1 infection that the potential risks of breastfeeding include: (1) HIV-1 transmission (in HIV-1–negative infants), (2) developing viral resistance (in HIV-1–positive infants), and (3) adverse reactions in a breastfed infant similar to those seen in adults [see Use in Specific Populations (8.2)] .

Administration Instructions

To avoid a dosing error from using the wrong formulation of dolutegravir, strongly advise patients and caregivers to visually inspect the tablets to verify the correct formulation each time the prescription is filled [see Dosage and Administration (2), Warnings and Precautions (5.5), How Supplied/Storage and Handling (16)] .

Inform patients and caregivers that TIVICAY PD tablets for oral suspension may be swallowed whole or dispersed in drinking water and should not be chewed, cut or crushed. The amount of water needed to disperse the tablet will depend on the dose (number of tablets prescribed).

Instruct patients and caregivers that if a dose of TIVICAY or TIVICAY PD is missed, to take it as soon as they remember. Advise patients and caregivers not to double the next dose or take more than the prescribed dose [see Dosage and Administration (2)] .

Storage

Instruct patients and caregivers to store the TIVICAY 10-mg tablets and TIVICAY PD 5-mg tablets for oral suspension in the original package, keep the bottle tightly closed, and protect from moisture. Do not remove desiccant [see How Supplied/Storage and Handling (16)] .

TIVICAY, TIVICAY PD, EPZICOM, JULUCA, and TRIUMEQ are trademarks owned by or licensed to the ViiV Healthcare group of companies.

The other brands listed are trademarks owned by or licensed to their respective owners and are not owned by or licensed to the ViiV Healthcare group of companies. The makers of these brands are not affiliated with and do not endorse the ViiV Healthcare group of companies or its products.

Manufactured for:

ViiV Healthcare

Durham, NC 27701

©2025 ViiV Healthcare group of companies or its licensor.

TVC:20PI

PHARMACIST‑DETACH HERE AND GIVE INSTRUCTIONS TO PATIENT
_ _ _ _ _ _ _ _ _ _ _ _ _ _ _ _ _ _ _ _ _ _ _ _ _ _ _ _ _ _ _ _ _ _ _ _ _ _ _ _ _ _ _ _ _ _ _ _ _ _ _ _ _

PATIENT INFORMATION

TIVICAY (TIV-eh-kay)

(dolutegravir)

tablets

TIVICAY PD (TIV-eh-kay Pe De)

(dolutegravir)

tablets for oral suspension

What is TIVICAY and TIVICAY PD?

TIVICAY and TIVICAY PD are prescription medicines used to treat Human Immunodeficiency Virus-1 (HIV-1) infection together with:

- other HIV-1 medicines in adults who have not received HIV-1 medicines in the past or to replace their current HIV-1 medicines.
- other HIV-1 medicines in children, aged at least 4 weeks and weighing at least 6.6 pounds (3 kg), who have not received HIV-1 medicines in the past or to replace their current HIV-1 medicines when their healthcare provider determines that they meet certain requirements.

TIVICAY is used together with rilpivirine as a complete regimen to treat Human Immunodeficiency Virus-1 (HIV-1) infection in adults to replace their current HIV-1 medicines when their healthcare provider determines that they meet certain requirements.

HIV-1 is the virus that causes Acquired Immune Deficiency Syndrome (AIDS).

It is not known if TIVICAY or TIVICAY PD is safe and effective in children who are less than 4 weeks of age and weigh less than 6.6 pounds (3 kg) or in children who have received certain types of medicine for HIV-1 infection.

Do not take TIVICAY or TIVICAY PD if you:

- have ever had an allergic reaction to a medicine that contains dolutegravir.
- take dofetilide.

Before you take TIVICAY or TIVICAY PD, tell your healthcare provider about all of your medical conditions, including if you:

- have or have had liver problems, including hepatitis B or C infection.
- are pregnant or plan to become pregnant. Talk to your healthcare provider about the benefits and risks of treatment with TIVICAY or TIVICAY PD during pregnancy.

Pregnancy Registry.There is a pregnancy registry for those who take TIVICAY or TIVICAY PD during pregnancy. The purpose of this registry is to collect information about the health of you and your baby. Talk with your healthcare provider about how you can take part in this registry.

- are breastfeeding or plan to breastfeed. TIVICAY and TIVICAY PD pass to your baby in your breast milk. Talk with your healthcare provider about the following risks to your baby from breastfeeding during treatment with TIVICAY and TIVICAY PD:
  - the HIV-1 virus may pass to your baby if your baby does not have HIV-1 infection.
  - the HIV-1 virus may become harder to treat if your baby has HIV-1 infection.
  - your baby may get side effects from TIVICAY.

Tell your healthcare provider about all the medicines you take,including prescription and over-the-counter medicines, vitamins, and herbal supplements.

Some medicines interact with TIVICAY or TIVICAY PD. Keep a list of your medicines and show it to your healthcare provider and pharmacist when you get a new medicine.

- You can ask your healthcare provider or pharmacist for a list of medicines that interact with TIVICAY or TIVICAY PD.
- Do not start taking a new medicine without telling your healthcare provider.Your healthcare provider can tell you if it is safe to take TIVICAY or TIVICAY PD with other medicines.

How should I take TIVICAY or TIVICAY PD?

- Take TIVICAY or TIVICAY PD exactly as your healthcare provider tells you to take it.
- Take TIVICAY or TIVICAY PD with or without food.
- For children who cannot swallow tablets, read the Instructions for Use at the end of this patient information for detailed instructions on how to prepare a dose of TIVICAY PD tablets for oral suspension.
- TIVICAY PD may be swallowed whole or dispersed in drinking water and should not be chewed, cut, or crushed.
- TIVICAY tablets are not the same as TIVICAY PD tablets for oral suspension and cannot be substituted for each other. Check to make sure you receive the correct form of TIVICAY each time you or your child’s prescription is filled to avoid using the wrong medicine.
- Do not change your dose, switch medicines or stop taking TIVICAY or TIVICAY PD without talking with your healthcare provider first.
- If you take antacids, laxatives, or other medicines that contain aluminum, magnesium, or buffered medicines, TIVICAY or TIVICAY PD should be taken at least 2 hours before or 6 hours after you take these medicines.
- If you need to take iron or calcium supplements by mouth during treatment with TIVICAY or TIVICAY PD:
  - If you take TIVICAY with food, you may take these supplements at the same time that you take TIVICAY.
  - If you do not take TIVICAY or TIVICAY PD with food, take TIVICAY or TIVICAY PD at least 2 hours before or 6 hours after you take these supplements.
- Do not miss a dose of TIVICAY or TIVICAY PD.
- If you miss a dose of TIVICAY or TIVICAY PD, take it as soon as you remember. Do not take 2 doses at the same time or take more than your prescribed dose.
- Stay under the care of a healthcare provider during treatment with TIVICAY or TIVICAY PD.
- Do not run out of TIVICAY or TIVICAY PD. The virus in your blood may increase and the virus may become harder to treat. When your supply starts to run low, get more from your healthcare provider or pharmacy.
- If you take too much TIVICAY or TIVICAY PD, call your healthcare provider or go to the nearest hospital emergency room right away.

What are the possible side effects of TIVICAY or TIVICAY PD?

- TIVICAY or TIVICAY PD can cause serious side effects including:
- Allergic reactions.Call your healthcare provider right away if you develop a rash with TIVICAY or TIVICAY PD. Stop taking TIVICAY or TIVICAY PD and get medical help right away if you develop a rash with any of the following signs or symptoms:

- fever
- generally ill feeling
- tiredness
- muscle or joint aches
- blisters or sores in mouth

- blisters or peeling of the skin
- redness or swelling of the eyes
- swelling of the mouth, face, lips, or tongue
- problems breathing

- Liver problems.People with a history of hepatitis B or C virus may have an increased risk of developing new or worsening changes in certain liver tests during treatment with TIVICAY or TIVICAY PD. Liver problems, including liver failure, have also happened in people without a history of liver disease or other risk factors. Your healthcare provider may do blood tests to check your liver. Call your healthcare provider right away if you develop any of the following signs or symptoms of liver problems:

- your skin or the white part of your eyes turns yellow (jaundice)
- dark or “tea-colored” urine
- light-colored stools (bowel movements)

- nausea or vomiting
- loss of appetite
- pain, aching, or tenderness on the right side of your stomach area

- Changes in your immune system (Immune Reconstitution Syndrome)can happen when you start taking HIV-1 medicines. Your immune system may get stronger and begin to fight infections that have been hidden in your body for a long time. Tell your healthcare provider right away if you start having new symptoms after you start taking TIVICAY or TIVICAY PD.
- The most common side effects of TIVICAY include:

- trouble sleeping

- tiredness

- headache

These are not all the possible side effects of TIVICAY or TIVICAY PD. Call your doctor for medical advice about side effects. You may report side effects to FDA at 1‑800‑FDA‑1088.

How should I store TIVICAY or TIVICAY PD?

- Store TIVICAY 10-mg, 25-mg, and 50-mg tablets at room temperature between 68°F to 77°F (20°C to 25°C).
- Store TIVICAY 10-mg tablets in the original bottle. Keep the bottle tightly closed and protected from moisture. The bottle contains a desiccant packet to help keep your medicine dry (protect it from moisture). Do not remove the desiccant packet from the bottle.
- Store TIVICAY PD 5-mg tablets for oral suspension at room temperature below 86°F (30°C) in the original bottle. Keep the bottle tightly closed and protected from moisture. The bottle contains a desiccant packet to help keep your medicine dry (protect it from moisture). Do not remove the desiccant packet from the bottle.

Keep TIVICAY, TIVICAY PD, and all medicines out of the reach of children.

General information about the safe and effective use of TIVICAY or TIVICAY PD.

Medicines are sometimes prescribed for purposes other than those listed in a Patient Information leaflet. Do not use TIVICAY or TIVICAY PD for a condition for which it was not prescribed. Do not give TIVICAY or TIVICAY PD to other people, even if they have the same symptoms you have. It may harm them. You can ask your healthcare provider or pharmacist for information about TIVICAY that is written for health professionals.

What are the ingredients in TIVICAY and TIVICAY PD?

Active ingredient:dolutegravir.

Inactive ingredients:

TIVICAY tablets: D-mannitol, microcrystalline cellulose, povidone K29/32, sodium starch glycolate, and sodium stearyl fumarate. The tablet film‑coating contains the inactive ingredients iron oxide yellow (for the 25-mg and 50-mg tablets only), macrogol/PEG, polyvinyl alcohol-part hydrolyzed, talc, and titanium dioxide.

TIVICAY PD tablets for oral suspension: calcium sulfate dihydrate, crospovidone, mannitol, microcrystalline cellulose, povidone K29/32, silicified microcrystalline cellulose, sodium starch glycolate, strawberry cream flavor, sucralose, and sodium stearyl fumarate. The tablet film-coating contains hypromellose, polyethylene glycol, and titanium dioxide.

Manufactured for:

ViiV Healthcare

Durham, NC 27701

TIVICAY and TIVICAY PD are trademarks owned by or licensed to the ViiV Healthcare group of companies.

©2024 ViiV Healthcare group of companies or its licensor.

TVC:14PIL

For more information, go to www.TIVICAY.comor call 1-877-844-8872.

This Patient Information has been approved by the U.S. Food and Drug Administration.

Revised: 4/2024

INSTRUCTIONS FOR USE

TIVICAY PD (TIV-eh-kay Pe De)

(dolutegravir) tablets for oral suspension

5 mg

Read this Instructions for Use before giving a dose of medicine.

Follow the steps below, using clean drinking water to prepare and give a dose to an infant or a child who cannot swallow the tablets.

Important information

Always give this medicine exactly as your healthcare provider tells you. Talk to your healthcare provider if you are not sure.

Do notchew, cut, or crush the tablets.

If you forget to give a dose of medicine, give it as soon as you remember. Do not give 2 doses at the same time or give more than your healthcare provider has prescribed.

If your child does not or cannot take the full dose, call your healthcare provider.

If you give too much medicine, get emergency medical help right away.

If your child is able and prefers to swallow the tablets, then you may skip the following steps.

Your pack contains:

- A bottle containing 60 TIVICAY PDtablets for oral suspension.
- Dosing kit:
  - Cup:Use this to prepare and give the medicine to children.
  - Syringe:Use this to give the medicine to infants.

You will also need:

- Clean drinking water.

Getting Ready

Step 1. Pour water

Figure A

- Pour clean drinking water into the cup.
  The Water Volume Guide in Figure A shows the amount of water needed for the prescribed dose.
  See Figure A.

Use drinking water only.

Do notuse any other drink or food to prepare the dose.

Step 2. Prepare the medicine

Figure B Figure C

- Add the prescribed number of tablet(s) to the water. See Figure B.
- Swirl the cup gently for 1 to 2 minutes to disperse the tablet(s). The medicine will become cloudy. Take care not to spill any of the medicine. See Figure C.
- Check that the medicine is ready. If there are any lumps of tablet, swirl the cup until they are gone.

If you spill any medicine, clean up the spill.

Throw away the rest of the prepared medicine and make a new dose.

You must give the dose of medicine within 30 minutes of preparing the dose.If it has been more than 30 minutes, wash away all the dose in the cup using water and prepare a new dose of medicine.

Giving the medicine

Step 3. Give the medicine

Figure D

- Make sure that the child is upright. Give all the prepared medicine to the child. See Figure D.
- Add another 5 mL of drinking water to the cup, swirl, and give it all to the child.
- Repeat if any medicine remains in the cup to make sure the child gets the full dose.

Figure E Figure F

- Place the tip of the syringe into the prepared medicine and draw up all the medicine into the syringe by pulling up on the plunger. See Figure E.
- Place the tip of the syringe against the inside of the infant’s cheek. Gently push down the plunger to give the dose slowly. See Figure F.
- Add another 5 mL of drinking water to the cup and swirl. Draw up the remaining medicine into the syringe and give it all to the infant.
- Repeat if any medicine remains in the syringe to make sure the infant gets the full dose.

Allow time for the medicine to be swallowed .

Cleaning

Step 4. Clean the dosing items

Figure G Figure H

- Wash the cup with water. See Figure G.
- Pull the plunger out of the syringe and wash the syringe parts separately in water. Allow parts to dry completely before reassembling and storing. See Figure H.
- All parts will need to be clean before preparing the next dose.

Storage Information

Store TIVICAY PD tablets for oral suspension at room temperature below 86°F (30°C) in the original bottle. Keep the bottle tightly closed and protect from moisture. The bottle contains a desiccant packet to help keep your medicine dry (protect it from moisture). Do not remove the desiccant packet from the bottle.

Keep TIVICAY PD and all medicines out of the reach of children.

Disposal Information

When all the tablets in the bottle have been taken or are no longer needed, throw away the bottle, cup, and syringe. Dispose of them using your local household waste guidelines.

You will get a new cup and syringe in your next pack.

Manufactured for:

ViiV Healthcare

Durham, NC 27701

Trademarks are owned by or licensed to the ViiV Healthcare group of companies.

©2024 ViiV Healthcare group of companies or its licensor.

TVC: 3IFU

This Instructions for Use has been approved by the U.S. Food and Drug Administration.

Revised: 4/2024